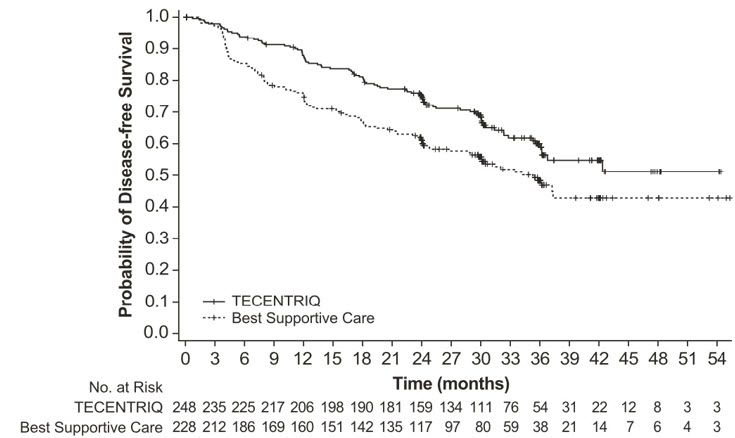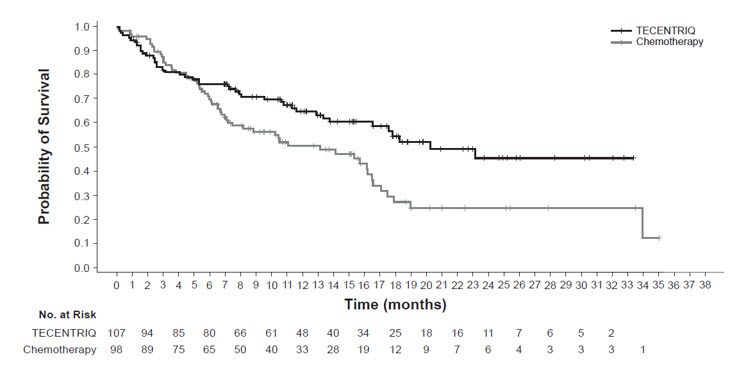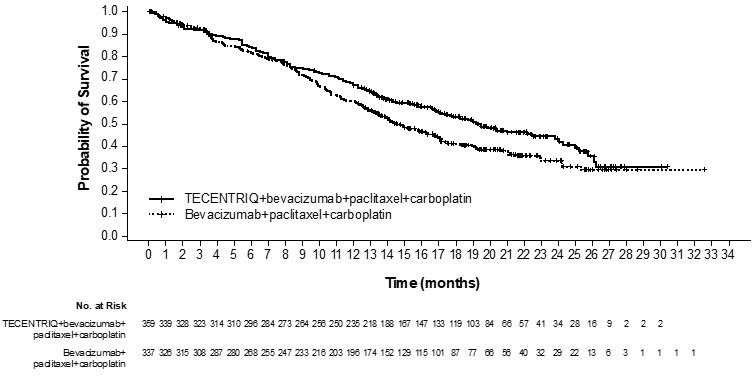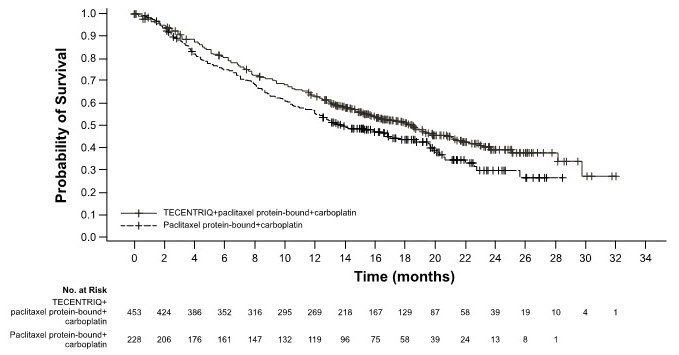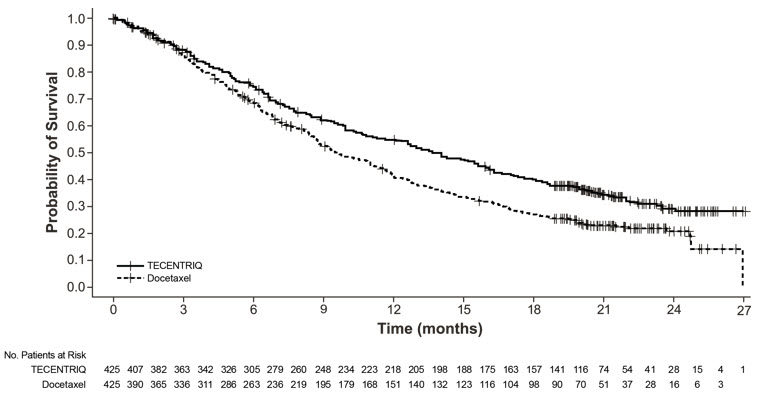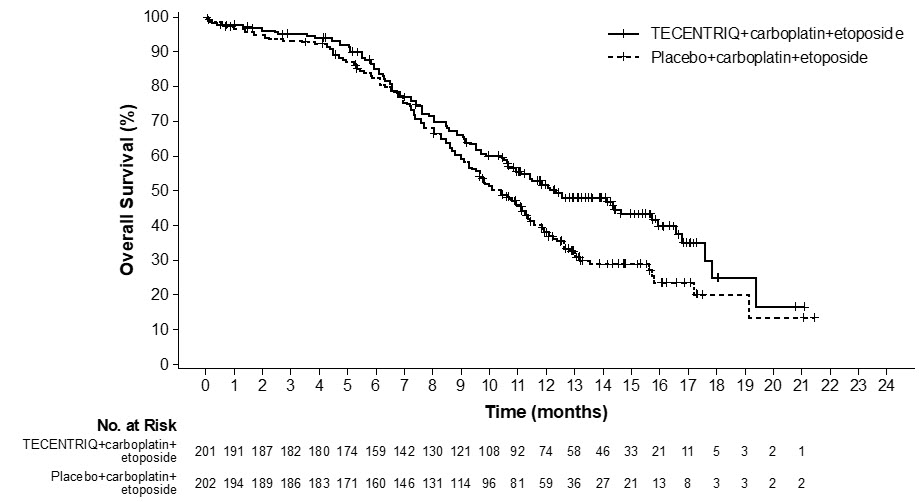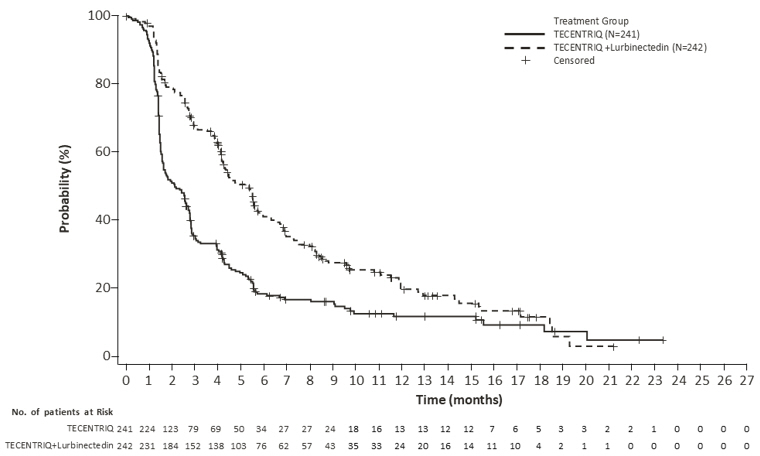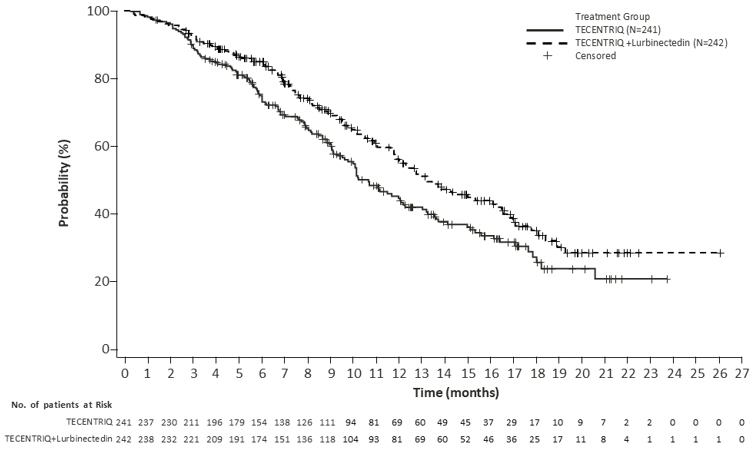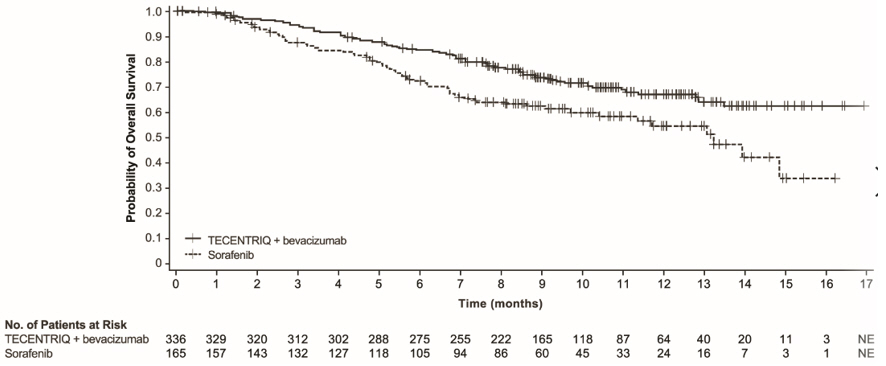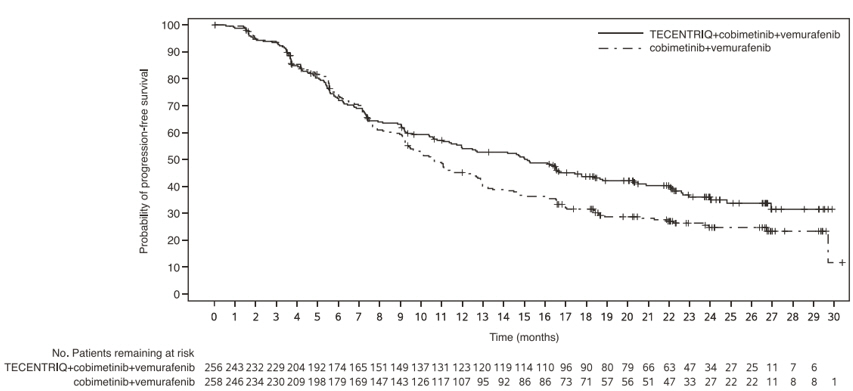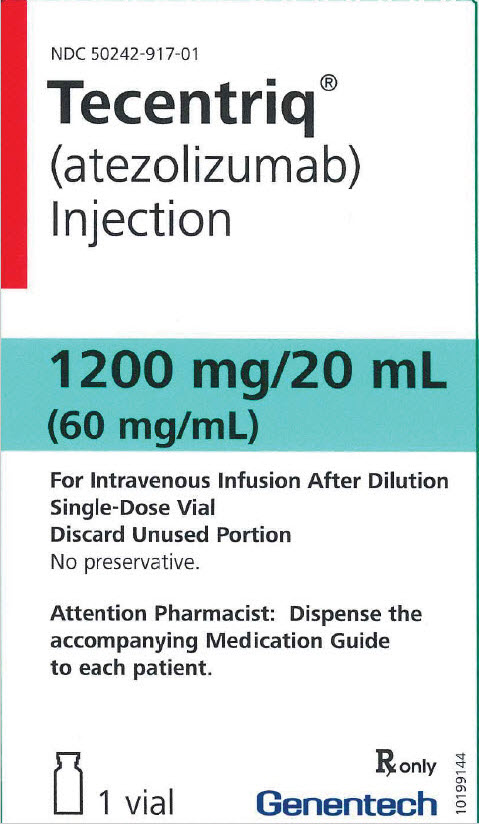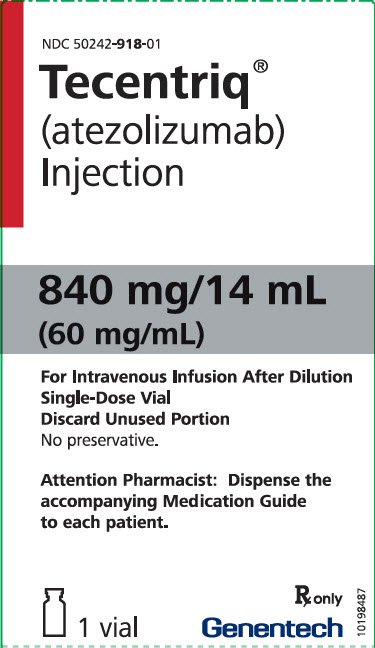 DRUG LABEL: TECENTRIQ
NDC: 50242-917 | Form: INJECTION, SOLUTION
Manufacturer: Genentech, Inc.
Category: prescription | Type: HUMAN PRESCRIPTION DRUG LABEL
Date: 20251125

ACTIVE INGREDIENTS: ATEZOLIZUMAB 1200 mg/20 mL
INACTIVE INGREDIENTS: HISTIDINE 62 mg/20 mL; ACETIC ACID 16.5 mg/20 mL; SUCROSE 821.6 mg/20 mL; POLYSORBATE 20 8 mg/20 mL; WATER

HIGHLIGHTS OF PRESCRIBING INFORMATION

These highlights do not include all the information needed to use TECENTRIQ safely and effectively. See full prescribing information for TECENTRIQ.
TECENTRIQ® (atezolizumab) injection, for intravenous use
Initial U.S. Approval: 2016

RECENT MAJOR CHANGES

Warnings and Precautions (5.2) | 08/2025
Indications and Usage (1.2) | 10/2025

1 INDICATIONS AND USAGE

TECENTRIQ is a programmed death-ligand 1 (PD-L1) blocking antibody indicated:

Non-Small Cell Lung Cancer (NSCLC)

- as adjuvant treatment following resection and platinum-based chemotherapy for adult patients with Stage II to IIIA NSCLC whose tumors have PD-L1 expression on ≥ 1% of tumor cells, as determined by an FDA-approved test. (1.1, 14.1)
- for the first-line treatment of adult patients with metastatic NSCLC whose tumors have high PD-L1 expression (PD-L1 stained ≥ 50% of tumor cells [TC ≥ 50%] or PD-L1 stained tumor-infiltrating immune cells [IC] covering ≥ 10% of the tumor area [IC ≥ 10%]), as determined by an FDA-approved test, with no EGFR or ALK genomic tumor aberrations. (1.1)
- in combination with bevacizumab, paclitaxel, and carboplatin, for the first-line treatment of adult patients with metastatic non-squamous NSCLC with no EGFR or ALK genomic tumor aberrations. (1.1)
- in combination with paclitaxel protein-bound and carboplatin for the first-line treatment of adult patients with metastatic non-squamous NSCLC with no EGFR or ALK genomic tumor aberrations (1.1)
- for the treatment of adult patients with metastatic NSCLC who have disease progression during or following platinum-containing chemotherapy. Patients with EGFR or ALK genomic tumor aberrations should have disease progression on FDA-approved therapy for NSCLC harboring these aberrations prior to receiving TECENTRIQ. (1.1)

Small Cell Lung Cancer (SCLC)

- in combination with carboplatin and etoposide, for the first-line treatment of adult patients with extensive-stage small cell lung cancer (ES-SCLC). (1.2)
- in combination with lurbinectedin, for the maintenance treatment of adult patients with ES-SCLC whose disease has not progressed after first-line induction therapy with TECENTRIQ or atezolizumab and hyaluronidase-tqjs, carboplatin and etoposide. (1.2)

Hepatocellular Carcinoma (HCC)

- in combination with bevacizumab for the treatment of adult patients with unresectable or metastatic HCC who have not received prior systemic therapy. (1.3)

Melanoma

- in combination with cobimetinib and vemurafenib for the treatment of adult patients with BRAF V600 mutation-positive unresectable or metastatic melanoma. (1.4)

Alveolar Soft Part Sarcoma (ASPS)

- for the treatment of adult and pediatric patients 2 years of age and older with unresectable or metastatic ASPS. (1.5)

2 DOSAGE AND ADMINISTRATION

Administer TECENTRIQ intravenously over 60 minutes. If the first infusion is tolerated, all subsequent infusions may be delivered over 30 minutes.

NSCLC

- In the adjuvant setting, administer TECENTRIQ following resection and up to 4 cycles of platinum-based chemotherapy as 840 mg every 2 weeks, 1200 mg every 3 weeks or 1680 mg every 4 weeks for up to 1 year. (2.2)
- In the metastatic setting, administer TECENTRIQ as 840 mg every 2 weeks, 1200 mg every 3 weeks, or 1680 mg every 4 weeks. (2.2)
- When administering with chemotherapy with or without bevacizumab, administer TECENTRIQ prior to chemotherapy and bevacizumab when given on the same day. (2.2)

Small Cell Lung Cancer

- Administer TECENTRIQ as 840 mg every 2 weeks, 1200 mg every 3 weeks, or 1680 mg every 4 weeks. Administer TECENTRIQ prior to chemotherapy when given on the same day. (2.2)

Hepatocellular Carcinoma

- Administer TECENTRIQ as 840 mg every 2 weeks, 1200 mg every 3 weeks, or 1680 mg every 4 weeks. Administer TECENTRIQ prior to bevacizumab when given on the same day. Bevacizumab is administered at 15 mg/kg every 3 weeks. (2.2)

Melanoma

- Following completion of a 28-day cycle of cobimetinib and vemurafenib, administer TECENTRIQ 840 mg every 2 weeks, 1200 mg every 3 weeks, or 1680 mg every 4 weeks with cobimetinib 60 mg orally once daily (21 days on /7 days off) and vemurafenib 720 mg orally twice daily. (2.2)

ASPS

- Adults: Administer TECENTRIQ as 840 mg every 2 weeks, 1200 mg every 3 weeks, or 1680 mg every 4 weeks. (2.2)
- Pediatric patients 2 years of age and older: 15 mg/kg (up to a maximum of 1200 mg), every 3 weeks (2.2)

3 DOSAGE FORMS AND STRENGTHS

Injection: 840 mg/14 mL (60 mg/mL) and 1200 mg/20 mL (60 mg/mL) solution in a single-dose vial. (3)

4 CONTRAINDICATIONS

None. (4)

5 WARNINGS AND PRECAUTIONS

- Immune-Mediated Adverse Reactions
  - Immune-mediated adverse reactions, which may be severe or fatal, can occur in any organ system or tissue, including the following: immune-mediated pneumonitis, immune-mediated colitis, immune-mediated hepatitis, immune-mediated endocrinopathies, immune-mediated dermatologic adverse reactions, immune-mediated nephritis and renal dysfunction, and solid organ transplant rejection. (5.1)
  - Monitor for early identification and management. Evaluate liver enzymes, creatinine, and thyroid function at baseline and periodically during treatment. (5.1)
  - Withhold or permanently discontinue based on severity and type of reaction. (5.1).
- Infusion-Related Reactions: Interrupt, slow the rate of infusion, or permanently discontinue based on severity of infusion reactions. (5.2)
- Complications of Allogeneic HSCT: Fatal and other serious complications can occur in patients who receive allogeneic HSCT before or after being treated with a PD-1/PD-L1 blocking antibody. (5.3)
- Embryo-Fetal Toxicity: Can cause fetal harm. Advise females of reproductive potential of the potential risk to a fetus and use of effective contraception. (5.4, 8.1, 8.3)

6 ADVERSE REACTIONS

TECENTRIQ as a single-agent

- Most common adverse reactions (≥ 20%) with TECENTRIQ as a single-agent are fatigue/asthenia, decreased appetite, nausea, cough, and dyspnea. (6.1)

TECENTRIQ in combination with other antineoplastic drugs

- Most common adverse reactions (≥ 20%) in patients with NSCLC and SCLC are fatigue/asthenia, nausea, alopecia, constipation, diarrhea, and decreased appetite. (6.1)

TECENTRIQ in combination with bevacizumab

- Most common adverse reactions (≥ 20%) in patients with HCC are hypertension, fatigue and proteinuria. (6.1)

TECENTRIQ in combination with cobimetinib and vemurafenib

- Most common adverse reactions (≥ 20%) with TECENTRIQ in patients with melanoma are rash, musculoskeletal pain, fatigue, hepatotoxicity, pyrexia, nausea, pruritus, edema, stomatitis, hypothyroidism, and photosensitivity reaction. (6.1)

To report SUSPECTED ADVERSE REACTIONS, contact Genentech at 1-888-835-2555 or FDA at 1-800-FDA-1088 or www.fda.gov/medwatch.

8 USE IN SPECIFIC POPULATIONS

Lactation: Advise not to breastfeed. (8.2)

FULL PRESCRIBING INFORMATION

1 INDICATIONS AND USAGE

1.1 Non-Small Cell Lung Cancer

- TECENTRIQ, as a single-agent, is indicated as adjuvant treatment following resection and platinum-based chemotherapy for adult patients with stage II to IIIA [see Clinical Studies (14.1)] non-small cell lung cancer (NSCLC) whose tumors have PD-L1 expression on ≥ 1% of tumor cells, as determined by an FDA-approved test [see Dosage and Administration (2.1)].
- TECENTRIQ, as a single agent, is indicated for the first-line treatment of adult patients with metastatic non-small cell lung cancer (NSCLC) whose tumors have high PD-L1 expression (PD-L1 stained ≥ 50% of tumor cells [TC ≥ 50%] or PD-L1 stained tumor-infiltrating immune cells [IC] covering ≥ 10% of the tumor area [IC ≥ 10%]), as determined by an FDA-approved test, with no EGFR or ALK genomic tumor aberrations [see Dosage and Administration (2.1)].
- TECENTRIQ, in combination with bevacizumab, paclitaxel, and carboplatin, is indicated for the first-line treatment of adult patients with metastatic non-squamous NSCLC with no EGFR or ALK genomic tumor aberrations.
- TECENTRIQ, in combination with paclitaxel protein-bound and carboplatin, is indicated for the first-line treatment of adult patients with metastatic non-squamous NSCLC with no EGFR or ALK genomic tumor aberrations.
- TECENTRIQ, as a single-agent, is indicated for the treatment of adult patients with metastatic NSCLC who have disease progression during or following platinum-containing chemotherapy. Patients with EGFR or ALK genomic tumor aberrations should have disease progression on FDA-approved therapy for NSCLC harboring these aberrations prior to receiving TECENTRIQ.

1.2 Small Cell Lung Cancer

- TECENTRIQ, in combination with carboplatin and etoposide, is indicated for the first-line treatment of adult patients with extensive-stage small cell lung cancer (ES-SCLC).
- TECENTRIQ, in combination with lurbinectedin, is indicated for the maintenance treatment of adult patients with ES-SCLC whose disease has not progressed after first-line induction therapy with TECENTRIQ or atezolizumab and hyaluronidase-tqjs, carboplatin and etoposide.

1.3 Hepatocellular Carcinoma

TECENTRIQ, in combination with bevacizumab, is indicated for the treatment of adult patients with unresectable or metastatic hepatocellular carcinoma (HCC) who have not received prior systemic therapy.

1.4 Melanoma

TECENTRIQ, in combination with cobimetinib and vemurafenib, is indicated for the treatment of adult patients with BRAF V600 mutation-positive unresectable or metastatic melanoma [see Dosage and Administration (2.1)].

1.5 Alveolar Soft Part Sarcoma

TECENTRIQ, as a single agent, is indicated for the treatment of adult and pediatric patients 2 years of age and older with unresectable or metastatic alveolar soft part sarcoma (ASPS).

2 DOSAGE AND ADMINISTRATION

2.1 Patient Selection for Treatment of Non-Small Cell Lung Cancer and Melanoma

Select patients with Stage II to IIIA non-small cell lung cancer for treatment with TECENTRIQ as a single agent based on PD-L1 expression on tumor cells [see Clinical Studies (14.1)].

Select patients with first-line metastatic non-small cell lung cancer for treatment with TECENTRIQ as a single agent based on the PD-L1 expression on tumor cells or on tumor-infiltrating immune cells [see Clinical Studies (14.1)].

Information on FDA-approved tests for the determination of PD-L1 expression in metastatic non-small cell lung cancer are available at: http://www.fda.gov/CompanionDiagnostics.

Select patients with unresectable or metastatic melanoma for treatment with TECENTRIQ in combination with cobimetinib and vemurafenib after confirming the presence of a BRAF V600 mutation [see Clinical Studies (14.4)]. Information on FDA-approved tests for the detection of BRAF V600 mutations in melanoma is available at: http://www.fda.gov/CompanionDiagnostics.

2.2 Recommended Dosage

The recommended dosages of TECENTRIQ are presented in Table 1. Administer TECENTRIQ as an intravenous infusion over 60 minutes. If the first infusion is tolerated, all subsequent infusions may be delivered over 30 minutes.

Table 1: Recommended Dosage of TECENTRIQ as a Single Agent
Indication | Recommended Dosage of TECENTRIQ | Duration of Therapy
Metastatic NSCLC | - 840 mg every 2 weeks or - 1200 mg every 3 weeks or - 1680 mg every 4 weeks | Until disease progression or unacceptable toxicity
Adjuvant Treatment of NSCLC | - 840 mg every 2 weeks or - 1200 mg every 3 weeks or - 1680 mg every 4 weeks | Up to one year, unless there is disease recurrence or unacceptable toxicity
ASPS (adult) | - 840 mg every 2 weeks or - 1200 mg every 3 weeks or - 1680 mg every 4 weeks | Until disease progression or unacceptable toxicity
ASPS (pediatric, 2 years of age and older) | 15 mg/kg (up to a maximum 1200 mg) every 3 weeks | Until disease progression or unacceptable toxicity

The recommended intravenous dosages of TECENTRIQ in combination with other therapeutic agents are presented in Table 2. Refer to the respective Prescribing Information for each therapeutic agent administered in combination with TECENTRIQ for the recommended dosage information, as appropriate.

Table 2: Recommended Dosage of TECENTRIQ in Combination with Other Therapeutic Agents
Indication | Recommended Dosage of TECENTRIQ | Duration of Therapy
NSCLC | - 840 mg every 2 weeks or - 1200 mg every 3 weeks or - 1680 mg every 4 weeks; Administer TECENTRIQ prior to chemotherapy and bevacizumab when given on the same day. | Until disease progression or unacceptable toxicity
SCLC | - 840 mg every 2 weeks or - 1200 mg every 3 weeks or - 1680 mg every 4 weeks; Administer TECENTRIQ prior to chemotherapy when given on the same day. | Until disease progression or unacceptable toxicity
HCC | - 840 mg every 2 weeks or - 1200 mg every 3 weeks or - 1680 mg every 4 weeks; Administer TECENTRIQ prior to bevacizumab when given on the same day. Bevacizumab is administered at 15 mg/kg every 3 weeks. | Until disease progression or unacceptable toxicity
Melanoma | - 840 mg every 2 weeks or - 1200 mg every 3 weeks or - 1680 mg every 4 weeks; Administer TECENTRIQ with cobimetinib 60 mg orally once daily (21 days on and 7 days off) and vemurafenib 720 mg orally twice daily. Prior to initiating TECENTRIQ, patients should receive a 28-day treatment cycle of cobimetinib 60 mg orally once daily (21 days on and 7 days off) and vemurafenib 960 mg orally twice daily from Days 1-21 and vemurafenib 720 mg orally twice daily from Days 22-28. | Until disease progression or unacceptable toxicity

2.3 Dosage Modifications for Adverse Reactions

No dose reduction for TECENTRIQ is recommended. In general, withhold TECENTRIQ for severe (Grade 3) immune-mediated adverse reactions. Permanently discontinue TECENTRIQ for life-threatening (Grade 4) immune-mediated adverse reactions, recurrent severe (Grade 3) immune-mediated reactions that require systemic immunosuppressive treatment, or an inability to reduce corticosteroid dose to 10 mg or less of prednisone or equivalent per day within 12 weeks of initiating steroids.

Dosage modifications for TECENTRIQ for adverse reactions that require management different from these general guidelines are summarized in Table 3.

Table 3: Recommended Dosage Modifications for Adverse Reactions
Adverse Reaction | Severity [Based on Common Terminology Criteria for Adverse Events (CTCAE), version 4] | Dosage Modification
Immune-Mediated Adverse Reactions [see Warnings and Precautions (5.1)]
Pneumonitis | Grade 2 | Withhold [Resume in patients with complete or partial resolution (Grade 0 to 1) after corticosteroid taper. Permanently discontinue if no complete or partial resolution within 12 weeks of initiating steroids or inability to reduce prednisone to 10 mg per day or less (or equivalent) within 12 weeks of initiating steroids]
Pneumonitis | Grades 3 or 4 | Permanently discontinue
Colitis | Grades 2 or 3 | Withhold
Colitis | Grade 4 | Permanently discontinue
Hepatitis with no tumor involvement of the liver | AST or ALT increases to more than 3 and up to 8 times ULN or Total bilirubin increases to more than 1.5 and up to 3 times ULN | Withhold
Hepatitis with no tumor involvement of the liver | AST or ALT increases to more than 8 times ULN or Total bilirubin increases to more than 3 times ULN | Permanently discontinue
Hepatitis with tumor involvement of the liver [If AST and ALT are less than or equal to ULN at baseline, withhold or permanently discontinue TECENTRIQ based on recommendations for hepatitis with no liver involvement] | Baseline AST or ALT is more than 1 and up to 3 times ULN and increases to more than 5 and up to 10 times ULN or Baseline AST or ALT is more than 3 and up to 5 times ULN and increases to more than 8 and up to 10 times ULN | Withhold
Hepatitis with tumor involvement of the liver [If AST and ALT are less than or equal to ULN at baseline, withhold or permanently discontinue TECENTRIQ based on recommendations for hepatitis with no liver involvement] | AST or ALT increases to more than 10 times ULN or Total bilirubin increases to more than 3 times ULN | Permanently discontinue
Endocrinopathies | Grades 3 or 4 | Withhold until clinically stable or permanently discontinue depending on severity
Nephritis with Renal Dysfunction | Grades 2 or 3 increased blood creatinine | Withhold
Nephritis with Renal Dysfunction | Grade 4 increased blood creatinine | Permanently discontinue
Exfoliative Dermatologic Conditions | Suspected SJS, TEN, or DRESS | Withhold
Exfoliative Dermatologic Conditions | Confirmed SJS, TEN, or DRESS | Permanently discontinue
Myocarditis or Pericarditis | Grades 2, 3, or 4 | Permanently discontinue
Neurological Toxicities | Grade 2 | Withhold
Neurological Toxicities | Grades 3 or 4 | Permanently discontinue
Other Adverse Reactions
Infusion-Related Reactions [see Warnings and Precautions (5.2)] | Grades 1 or 2 | Interrupt or slow the rate of infusion
Infusion-Related Reactions [see Warnings and Precautions (5.2)] | Grades 3 or 4 | Permanently discontinue
ALT = alanine aminotransferase, AST = aspartate aminotransferase, ULN = upper limit normal, DRESS = Drug Rash with Eosinophilia and Systemic Symptoms, SJS = Stevens Johnson syndrome, TEN = toxic epidermal necrolysis

2.4 Preparation and Administration

Preparation

Visually inspect drug product for particulate matter and discoloration prior to administration, whenever solution and container permit. Discard the vial if the solution is cloudy, discolored, or visible particles are observed. Do not shake the vial.

Prepare the solution for infusion as follows:

- Select the appropriate vial(s) based on the prescribed dose.
- Withdraw the required volume of TECENTRIQ from the vial(s) using sterile needle and syringe.
- Dilute to a final concentration between 3.2 mg/mL and 16.8 mg/mL in a polyvinyl chloride (PVC), polyethylene (PE), or polyolefin (PO) infusion bag containing 0.9% Sodium Chloride Injection, USP.
- Dilute with only 0.9% Sodium Chloride Injection, USP.
- Mix diluted solution by gentle inversion. Do not shake.
- Discard used or empty vials of TECENTRIQ.

Storage of Infusion Solution

This product does not contain a preservative.

Administer immediately once prepared. If diluted TECENTRIQ infusion solution is not used immediately, store solution either:

- At room temperature for no more than 6 hours from the time of preparation. This includes room temperature storage of the infusion in the infusion bag and time for administration of the infusion, or
- Under refrigeration at 2°C to 8°C (36°F to 46°F) for no more than 24 hours from time of preparation.

Do not freeze.

Do not shake.

Administration

Administer the initial infusion over 60 minutes through an intravenous line with or without a sterile, non-pyrogenic, low-protein binding in-line filter (pore size of 0.2–0.22 micron). If the first infusion is tolerated, all subsequent infusions may be delivered over 30 minutes.

Do not coadminister other drugs through the same intravenous line.

Do not administer as an intravenous push or bolus.

3 DOSAGE FORMS AND STRENGTHS

Injection: 840 mg/14 mL (60 mg/mL) and 1200 mg/20 mL (60 mg/mL) colorless to slightly yellow solution in a single-dose vial.

4 CONTRAINDICATIONS

None.

5 WARNINGS AND PRECAUTIONS

5.1 Severe and Fatal Immune-Mediated Adverse Reactions

TECENTRIQ is a monoclonal antibody that belongs to a class of drugs that bind to either the programmed death-receptor 1 (PD-1) or the PD-ligand 1 (PD-L1), blocking the PD-1/PD-L1 pathway, thereby removing inhibition of the immune response, potentially breaking peripheral tolerance and inducing immune-mediated adverse reactions. Important immune-mediated adverse reactions listed under Warnings and Precautions may not include all possible severe and fatal immune-mediated reactions.

Immune-mediated adverse reactions, which may be severe or fatal, can occur in any organ system or tissue. Immune-mediated adverse reactions can occur at any time after starting a PD-1/PD-L1 blocking antibody. While immune-mediated adverse reactions usually manifest during treatment with PD-1/PD-L1 blocking antibodies, immune-mediated adverse reactions can also manifest after discontinuation of PD-1/PD-L1 blocking antibodies.

Early identification and management of immune-mediated adverse reactions are essential to ensure safe use of PD-1/PD-L1 blocking antibodies. Monitor patients closely for symptoms and signs that may be clinical manifestations of underlying immune-mediated adverse reactions. Evaluate liver enzymes, creatinine, and thyroid function at baseline and periodically during treatment. In cases of suspected immune-mediated adverse reactions, initiate appropriate workup to exclude alternative etiologies, including infection. Institute medical management promptly, including specialty consultation as appropriate.

Withhold or permanently discontinue TECENTRIQ depending on severity [see Dosage and Administration (2.3)]. In general, if TECENTRIQ requires interruption or discontinuation, administer systemic corticosteroid therapy (1 to 2 mg/kg/day prednisone or equivalent) until improvement to Grade 1 or less. Upon improvement to Grade 1 or less, initiate corticosteroid taper and continue to taper over at least 1 month. Consider administration of other systemic immunosuppressants in patients whose immune-mediated adverse reactions are not controlled with corticosteroid therapy.

Toxicity management guidelines for adverse reactions that do not necessarily require systemic steroids (e.g., endocrinopathies and dermatologic reactions) are discussed below.

Immune-Mediated Pneumonitis

TECENTRIQ can cause immune-mediated pneumonitis. The incidence of pneumonitis is higher in patients who have received prior thoracic radiation.

TECENTRIQ as a Single Agent:

Immune-mediated pneumonitis occurred in 3% (83/2616) of patients receiving TECENTRIQ as a single agent, including fatal (<0.1%), Grade 4 (0.2%), Grade 3 (0.8%), and Grade 2 (1.1%) adverse reactions. Pneumonitis led to permanent discontinuation of TECENTRIQ in 0.5% and withholding of TECENTRIQ in 1.5% of patients.

Systemic corticosteroids were required in 55% (46/83) of patients with pneumonitis. Pneumonitis resolved in 69% of the 83 patients. Of the 39 patients in whom TECENTRIQ was withheld for pneumonitis, 25 reinitiated TECENTRIQ after symptom improvement; of these, 4% had recurrence of pneumonitis.

In IMpower010 immune-mediated pneumonitis occurred in 3.8% (19/495) of patients receiving TECENTRIQ as a single agent, including fatal (0.2%), Grade 4 (0.2%), and Grade 3 (0.6%) adverse reactions. Pneumonitis led to permanent discontinuation of TECENTRIQ in 2.2% and withholding of TECENTRIQ in 0.8% of patients.

Systemic corticosteroids were required in 63% (12/19) of patients with pneumonitis. Pneumonitis resolved in 84% of the 19 patients.

TECENTRIQ in Combination with Cobimetinib and Vemurafenib:

Immune-mediated pneumonitis occurred in 13% (29/230) of patients receiving TECENTRIQ in combination with cobimetinib and vemurafenib, including Grade 3 (1.3%) and Grade 2 (7%) adverse reactions. Pneumonitis led to permanent discontinuation of TECENTRIQ in 2.6% and withholding of TECENTRIQ in 7.4% of patients.

Systemic corticosteroids were required in 55% (16/29) of patients with pneumonitis. Pneumonitis resolved in 97% of the 29 patients. Of the 17 patients in whom TECENTRIQ was withheld for pneumonitis, 10 reinitiated TECENTRIQ after symptom improvement; of these, 50% had recurrence of pneumonitis.

Immune-Mediated Colitis

TECENTRIQ can cause immune-mediated colitis. Colitis can present with diarrhea, abdominal pain, and lower gastrointestinal (GI) bleeding. Cytomegalovirus (CMV) infection/reactivation has been reported in patients with corticosteroid-refractory immune-mediated colitis. In cases of corticosteroid-refractory colitis, consider repeating infectious workup to exclude alternative etiologies.

TECENTRIQ as a Single Agent:

Immune-mediated colitis occurred in 1% (26/2616) of patients receiving TECENTRIQ as a single agent, including Grade 3 (0.5%) and Grade 2 (0.3%) adverse reactions. Colitis led to permanent discontinuation of TECENTRIQ in 0.2% and withholding of TECENTRIQ in 0.5% of patients.

Systemic corticosteroids were required in 50% (13/26) of patients with colitis. Colitis resolved in 73% of the 26 patients. Of the 12 patients in whom TECENTRIQ was withheld for colitis, 8 reinitiated treatment with TECENTRIQ after symptom improvement; of these, 25% had recurrence of colitis.

Immune-Mediated Hepatitis

TECENTRIQ can cause immune-mediated hepatitis.

Immune-mediated hepatitis occurred in 1.8% (48/2616) of patients receiving TECENTRIQ as a single agent, including fatal (<0.1%), Grade 4 (0.2%), Grade 3 (0.5%), and Grade 2 (0.5%) adverse reactions. Hepatitis led to permanent discontinuation of TECENTRIQ in 0.2% and withholding of TECENTRIQ in 0.2% of patients.

Systemic corticosteroids were required in 25% (12/48) of patients with hepatitis. Hepatitis resolved in 50% of the 48 patients. Of the 6 patients in whom TECENTRIQ was withheld for hepatitis, 4 reinitiated treatment with TECENTRIQ after symptom improvement; of these, none had recurrence of hepatitis.

TECENTRIQ in Combination with Cobimetinib and Vemurafenib:

Immune-mediated hepatitis occurred in 6.1% (14/230) of patients receiving TECENTRIQ in combination with cobimetinib and vemurafenib, including Grade 4 (1.3%), Grade 3 (1.7%) and Grade 2 (1.3%) adverse reactions. Hepatitis led to permanent discontinuation of TECENTRIQ in 2.2% and withholding of TECENTRIQ in 1.7% of patients.

Systemic corticosteroids were required in 50% (7/14) of patients with hepatitis. Hepatitis resolved in 93% of the 14 patients. Of the 4 patients in whom TECENTRIQ was withheld for hepatitis, 3 reinitiated TECENTRIQ after symptom improvement; of these, 33% had recurrence of hepatitis.

Immune-Mediated Endocrinopathies

Adrenal Insufficiency

TECENTRIQ can cause primary or secondary adrenal insufficiency. For Grade 2 or higher adrenal insufficiency, initiate symptomatic treatment, including hormone replacement as clinically indicated. Withhold or permanently discontinue TECENTRIQ depending on severity [see Dosage and Administration (2.3)].

Adrenal insufficiency occurred in 0.4% (11/2616) of patients receiving TECENTRIQ as a single agent, including Grade 3 (<0.1%) and Grade 2 (0.2%) adverse reactions. Adrenal insufficiency led to permanent discontinuation of TECENTRIQ in one patient and withholding of TECENTRIQ in one patient.

Systemic corticosteroids were required in 82% (9/11) of patients with adrenal insufficiency; of these, 3 patients remained on systemic corticosteroids. The single patient in whom TECENTRIQ was withheld for adrenal insufficiency did not reinitiate TECENTRIQ.

In IMpower010 immune-mediated adrenal insufficiency occurred in 1.2% (6/495) of patients receiving TECENTRIQ as a single agent, including Grade 3 (0.4%) adverse reactions. Adrenal insufficiency led to permanent discontinuation of TECENTRIQ in 0.6% and withholding of TECENTRIQ in 0.2% of patients.

Systemic corticosteroids were required in 83% (5/6) of patients with adrenal insufficiency; of these, 4 patients remained on systemic corticosteroids.

Hypophysitis

TECENTRIQ can cause immune-mediated hypophysitis. Hypophysitis can present with acute symptoms associated with mass effect such as headache, photophobia, or visual field cuts. Hypophysitis can cause hypopituitarism. Initiate hormone replacement as clinically indicated. Withhold or permanently discontinue TECENTRIQ depending on severity [see Dosage and Administration (2.3)].

Hypophysitis occurred in <0.1% (2/2616) of patients receiving TECENTRIQ as a single agent, including Grade 2 (1 patient, <0.1%) adverse reactions. Hypophysitis led to permanent discontinuation of TECENTRIQ in one patient and no patients required withholding of TECENTRIQ.

Systemic corticosteroids were required in 50% (1/2) of patients with hypophysitis. Hypophysitis did not resolve in these 2 patients.

Thyroid disorders

TECENTRIQ can cause immune-mediated thyroid disorders. Thyroiditis can present with or without endocrinopathy. Hypothyroidism can follow hyperthyroidism. Initiate hormone replacement for hypothyroidism or medical management for hyperthyroidism as clinically indicated. Withhold or permanently discontinue TECENTRIQ depending on severity [see Dosage and Administration (2.3)].

Thyroiditis:

Thyroiditis occurred in 0.2% (4/2616) of patients receiving TECENTRIQ as a single agent, including Grade 2 (<0.1%) adverse reactions. Thyroiditis did not lead to permanent discontinuation of TECENTRIQ in any of these patients, but led to withholding of TECENTRIQ in one patient.

Hormone replacement therapy was required in 75% (3/4) of patients with thyroiditis. Systemic corticosteroids were required in 25% (1/4) of patients with thyroiditis. Thyroiditis resolved in 50% of patients. The single patient in whom TECENTRIQ was withheld for thyroiditis reinitiated TECENTRIQ; this patient did not have recurrence of thyroiditis.

In IMpower010, thyroiditis occurred in 1.2% (6/495) of patients receiving TECENTRIQ as a single agent, including Grade 2 (0.4%) adverse reactions. Thyroiditis led to withholding of TECENTRIQ in one patient.

Hormone replacement therapy was required in 67% (4/6) of patients with thyroiditis. Systemic corticosteroids were required in 33% (2/6) of patients with thyroiditis. Thyroiditis resolved in 50% of patients.

Hyperthyroidism:

TECENTRIQ as a Single Agent:

Hyperthyroidism occurred in 0.8% (21/2616) of patients receiving TECENTRIQ as a single agent, including Grade 2 (0.4%) adverse reactions. Hyperthyroidism did not lead to permanent discontinuation of TECENTRIQ in any of these patients, but led to withholding of TECENTRIQ in 0.1% of patients.

Antithyroid therapy was required in 29% (6/21) of patients with hyperthyroidism. Of these 6 patients, the majority remained on antithyroid treatment. Of the 3 patients in whom TECENTRIQ was withheld for hyperthyroidism, one patient reinitiated TECENTRIQ; this patient did not have recurrence of hyperthyroidism.

In IMpower010 hyperthyroidism occurred in 6% (32/495) of patients receiving TECENTRIQ as a single agent, including Grade 3 (0.4%) adverse reactions. Hyperthyroidism led to permanent discontinuation of TECENTRIQ in 0.8% and withholding of TECENTRIQ in 2.8% of patients.

Antithyroid therapy was required in 38% (12/32) of patients with hyperthyroidism. Of these 12 patients, the majority remained on antithyroid treatment. Of the 14 patients in whom TECENTRIQ was withheld for hyperthyroidism, 9 patients reinitiated TECENTRIQ.

TECENTRIQ in Combination with Cobimetinib and Vemurafenib:

Hyperthyroidism occurred in 19% (43/230) of patients receiving TECENTRIQ in combination with cobimetinib and vemurafenib, including Grade 3 (0.9%) and Grade 2 (7.8%) adverse reactions. Hyperthyroidism led to permanent discontinuation of TECENTRIQ in 0.4% and withholding of TECENTRIQ in 10% of patients.

Antithyroid therapy was required in 53% (23/43) of patients with hyperthyroidism. Of these 23 patients, the majority remained on antithyroid treatment. Of the 24 patients in whom TECENTRIQ was withheld for hyperthyroidism, 18 patients reinitiated TECENTRIQ; of these, 28% had recurrence of hyperthyroidism.

Hypothyroidism:

TECENTRIQ as a Single Agent:

Hypothyroidism occurred in 4.9% (128/2616) of patients receiving TECENTRIQ as a single agent, including Grade 3 (0.2%) and Grade 2 (3.4%) adverse reactions. Hypothyroidism did not lead to permanent discontinuation of TECENTRIQ in any of these patients, but led to withholding of TECENTRIQ in 0.6% of patients.

Hormone replacement therapy was required in 81% (104/128) of patients with hypothyroidism. The majority of patients with hypothyroidism remained on thyroid hormone replacement. Of the 17 patients in whom TECENTRIQ was withheld for hypothyroidism, 8 reinitiated TECENTRIQ after symptom improvement.

In IMpower010 hypothyroidism occurred in 17% (86/495) of patients receiving TECENTRIQ as a single agent. Hypothyroidism led to permanent discontinuation of TECENTRIQ in 1.6% and withholding of TECENTRIQ in 1.6% of patients.

Hormone replacement was required in 57% (49/86) of patients with hypothyroidism. The majority of patients with hypothyroidism remained on thyroid hormone replacement. Of the 8 patients in whom TECENTRIQ was withheld for hypothyroidism, 3 reinitiated TECENTRIQ after symptom improvement.

TECENTRIQ in Combination with Platinum-based Chemotherapy:

Hypothyroidism occurred in 11% (277/2421) of patients with NSCLC and SCLC receiving TECENTRIQ in combination with platinum-based chemotherapy, including Grade 4 (<0.1%), Grade 3 (0.3%), and Grade 2 (5.7%) adverse reactions. Hypothyroidism led to permanent discontinuation of TECENTRIQ in 0.1% and withholding of TECENTRIQ in 1.6% of patients.

Hormone replacement therapy was required in 71% (198/277) of patients with hypothyroidism. The majority of patients with hypothyroidism remained on thyroid hormone replacement. Of the 39 patients in whom TECENTRIQ was withheld for hypothyroidism, 9 reinitiated TECENTRIQ after symptom improvement.

TECENTRIQ in Combination with Cobimetinib and Vemurafenib:

Hypothyroidism occurred in 26% (60/230) of patients receiving TECENTRIQ in combination with cobimetinib and vemurafenib, including Grade 2 (9.1%) adverse reactions. Hypothyroidism did not lead to permanent discontinuation of TECENTRIQ in any of these patients, but led to withholding of TECENTRIQ in 2.6% of patients.

Hormone replacement therapy was required in 52% (31/60) of patients with hypothyroidism. The majority of patients with hypothyroidism remained on thyroid hormone replacement. Of the 6 patients in whom TECENTRIQ was withheld for hypothyroidism, 4 reinitiated TECENTRIQ after symptom improvement. The majority of patients with hypothyroidism required long term thyroid replacement.

Type 1 Diabetes Mellitus, which can present with Diabetic Ketoacidosis

Monitor patients for hyperglycemia or other signs and symptoms of diabetes. Initiate treatment with insulin as clinically indicated. Withhold or permanently discontinue TECENTRIQ depending on severity [see Dosage and Administration (2.3)].

Type 1 diabetes mellitus occurred in 0.3% (7/2616) of patients receiving TECENTRIQ, including Grade 3 (0.2%) and Grade 2 (<0.1%) adverse reactions. Type 1 diabetes mellitus led to permanent discontinuation of TECENTRIQ in one patient and withholding of TECENTRIQ in two patients.

Treatment with insulin was required for all patients with confirmed Type 1 diabetes mellitus and insulin therapy was continued long-term. Of the 2 patients in whom TECENTRIQ was withheld for Type 1 diabetes mellitus, both re-initiated TECENTRIQ treatment.

Immune-Mediated Nephritis with Renal Dysfunction

TECENTRIQ can cause immune-mediated nephritis.

TECENTRIQ as a Single Agent:

Immune-mediated nephritis with renal dysfunction occurred in <0.1% (1/2616) of patients receiving TECENTRIQ as a single agent, and this adverse reaction was a Grade 3 (<0.1%) adverse reaction. Nephritis led to permanent discontinuation of TECENTRIQ in this patient.

This patient required systemic corticosteroids. In this patient, nephritis did not resolve.

TECENTRIQ in Combination with Cobimetinib and Vemurafenib:

Immune-mediated nephritis with renal dysfunction occurred in 1.3% (3/230) of patients receiving TECENTRIQ in combination with cobimetinib and vemurafenib, including Grade 2 (1.3%) adverse reactions. Nephritis led to permanent discontinuation of TECENTRIQ in 0.4% and withholding of TECENTRIQ in 0.9% of patients.

Systemic corticosteroids were required in 67% (2/3) of patients with nephritis. Nephritis resolved in all 3 of these patients. Of the 2 patients in whom TECENTRIQ was withheld for nephritis, both reinitiated TECENTRIQ after symptom improvement and neither had recurrence of nephritis.

Immune-Mediated Dermatologic Adverse Reactions

TECENTRIQ can cause immune-mediated rash or dermatitis. Exfoliative dermatitis, including Stevens-Johnson syndrome (SJS), DRESS, and toxic epidermal necrolysis (TEN), has occurred with PD-1/PD-L1 blocking antibodies. Topical emollients and/or topical corticosteroids may be adequate to treat mild to moderate non-exfoliative rashes. Withhold or permanently discontinue TECENTRIQ depending on severity [see Dosage and Administration (2.3)].

Immune-mediated dermatologic adverse reactions occurred in 0.6% (15/2616) of patients receiving TECENTRIQ as a single agent, including Grade 3 (<0.1%) and Grade 2 (0.2%) adverse reactions. Dermatologic adverse reactions led to permanent discontinuation of TECENTRIQ in 0.1% and withholding of TECENTRIQ in 0.2% of patients.

Systemic corticosteroids were required in 20% (3/15) of patients with dermatologic adverse reactions. Dermatologic adverse reactions resolved in 87% of the 15 patients. Of the 4 patients in whom TECENTRIQ was withheld for immune-mediated dermatologic adverse reactions, none re-initiated TECENTRIQ.

Other Immune-Mediated Adverse Reactions

The following clinically significant immune-mediated adverse reactions occurred at an incidence of < 1% (unless otherwise noted) in patients who received TECENTRIQ or were reported with the use of other PD-1/PD-L1 blocking antibodies. Severe or fatal cases have been reported for some of these adverse reactions.

Cardiac/Vascular: Myocarditis, pericarditis, vasculitis.

Nervous System: Meningitis, encephalitis, myelitis and demyelination, myasthenic syndrome/myasthenia gravis (including exacerbation), Guillain-Barré syndrome, nerve paresis, autoimmune neuropathy.

Ocular: Uveitis, iritis, and other ocular inflammatory toxicities can occur. Some cases can be associated with retinal detachment. Various grades of visual impairment, including blindness, can occur. If uveitis occurs in combination with other immune-mediated adverse reactions, consider a Vogt-Koyanagi-Harada-like syndrome, as this may require treatment with systemic steroids to reduce the risk of permanent vision loss.

Gastrointestinal: Pancreatitis to include increases in serum amylase and lipase levels, gastritis, duodenitis.

Musculoskeletal and Connective Tissue: Myositis/polymyositis, rhabdomyolysis and associated sequelae including renal failure, arthritis, polymyalgia rheumatic.

Endocrine: Hypoparathyroidism.

Other (Hematologic/Immune): Hemolytic anemia, aplastic anemia, hemophagocytic lymphohistiocytosis, systemic inflammatory response syndrome, histiocytic necrotizing lymphadenitis (Kikuchi lymphadenitis), sarcoidosis, immune thrombocytopenic purpura, solid organ transplant rejection, other transplant (including corneal graft) rejection.

5.2 Infusion-Related Reactions

TECENTRIQ can cause severe or life-threatening infusion-related reactions, including anaphylaxis. Monitor for signs and symptoms of infusion-related reactions. Interrupt, slow the rate of, or permanently discontinue TECENTRIQ based on the severity [see Dosage and Administration (2.3)]. For Grade 1 or 2 infusion-related reactions, consider using pre-medications with subsequent doses.

In clinical studies enrolling 2616 patients with various cancers who received TECENTRIQ as a single-agent [see Adverse Reactions (6.1)], infusion-related reactions occurred in 1.3% of patients, including Grade 3 (0.2%). The frequency and severity of infusion-related reactions were similar whether TECENTRIQ was given as a single-agent in patients with various cancers, in combination with other antineoplastic drugs in NSCLC and SCLC, and across the recommended dose range (840 mg Q2W to 1680 mg Q4W).

5.3 Complications of Allogeneic HSCT after PD-1/PD-L1 Inhibitors

Fatal and other serious complications can occur in patients who receive allogeneic hematopoietic stem cell transplantation (HSCT) before or after being treated with a PD-1/PD-L1 blocking antibody. Transplant-related complications include hyperacute graft-versus-host disease (GVHD), acute GVHD, chronic GVHD, hepatic veno-occlusive disease (VOD) after reduced intensity conditioning, and steroid-requiring febrile syndrome (without an identified infectious cause). These complications may occur despite intervening therapy between PD-1/PD-L1 blockage and allogeneic HSCT.

Follow patients closely for evidence of transplant-related complications and intervene promptly. Consider the benefits versus risks of treatment with a PD-1/PD-L1 blocking antibody prior to or after an allogeneic HSCT.

5.4 Embryo-Fetal Toxicity

Based on its mechanism of action, TECENTRIQ can cause fetal harm when administered to a pregnant woman. There are no available data on the use of TECENTRIQ in pregnant women. Animal studies have demonstrated that inhibition of the PD-L1/PD-1 pathway can lead to increased risk of immune-related rejection of the developing fetus resulting in fetal death.

Verify pregnancy status of females of reproductive potential prior to initiating TECENTRIQ. Advise females of reproductive potential of the potential risk to a fetus. Advise females of reproductive potential to use effective contraception during treatment with TECENTRIQ and for at least 5 months after the last dose [see Use in Specific Populations (8.1, 8.3)].

6 ADVERSE REACTIONS

The following clinically significant adverse reactions are described elsewhere in the labeling:

- Severe and Fatal Immune-Mediated Adverse Reactions [see Warnings and Precautions (5.1)]
- Infusion-Related Reactions [see Warnings and Precautions (5.2)]
- Complications of Allogeneic HSCT after PD-1/PD-L1 Inhibitors [see Warnings and Precautions (5.3)]

6.1 Clinical Trials Experience

Because clinical trials are conducted under widely varying conditions, adverse reaction rates observed in the clinical trials of a drug cannot be directly compared to rates in the clinical trials of another drug and may not reflect the rates observed in practice.

The data described in WARNINGS AND PRECAUTIONS reflect exposure to TECENTRIQ as a single-agent in 2616 patients in two randomized, active-controlled studies (POPLAR, OAK) and three open-label, single arm studies (PCD4989g, BIRCH, FIR) which enrolled 1636 patients with metastatic NSCLC, and 980 patients with other tumor types. TECENTRIQ was administered at a dose of 1200 mg intravenously every 3 weeks in all studies except PCD4989g. Among the 2616 patients who received a single-agent TECENTRIQ, 36% were exposed for longer than 6 months and 20% were exposed for longer than 12 months. Using the dataset described for patients who received TECENTRIQ as a single-agent, the most common adverse reactions in ≥ 20% of patients were fatigue/asthenia (48%), decreased appetite (25%), nausea (24%), cough (22%), and dyspnea (22%). In addition, the data reflect exposure to TECENTRIQ as a single agent as adjuvant therapy in 495 patients with early-stage NSCLC enrolled in a randomized study (IMpower010).

In addition, the data reflect exposure to TECENTRIQ in combination with other antineoplastic drugs in 2421 patients with NSCLC (N = 2223) or SCLC (N = 198) enrolled in five randomized, active-controlled trials, including IMpower150, IMpower130 and IMpower133. Among the 2421 patients, 53% were exposed to TECENTRIQ for longer than 6 months and 29% were exposed to TECENTRIQ for longer than 12 months. Among the 2421 patients with NSCLC and SCLC who received TECENTRIQ in combination with other antineoplastic drugs, the most common adverse reactions in ≥20% of patients were fatigue/asthenia (49%), nausea (38%), alopecia (35%), constipation (29%), diarrhea (28%) and decreased appetite (27%).

The data also reflect exposure to TECENTRIQ administered in combination with cobimetinib and vemurafenib in 230 patients enrolled in IMspire150. Among the 230 patients, 62% were exposed to TECENTRIQ for longer than 6 months and 42% were exposed to TECENTRIQ for longer than 12 months.

Non-Small Cell Lung Cancer (NSCLC)

Adjuvant Treatment of Early-stage NSCLC

IMpower010

The safety of TECENTRIQ was evaluated in IMpower010, a multicenter, open-label, randomized trial for the adjuvant treatment of patients with stage IB (tumors ≥ 4 cm) - IIIA NSCLC who had complete tumor resection and received up to 4 cycles of cisplatin-based adjuvant chemotherapy. Patients received TECENTRIQ 1200 mg every 3 weeks (n=495) for 1 year (16 cycles), unless disease progression or unacceptable toxicity occurred, or best supportive care [see Clinical Studies (14.1)]. The median number of cycles received was 16 (range: 1, 16).

Fatal adverse reactions occurred in 1.8% of patients receiving TECENTRIQ; these included multiple organ dysfunction syndrome, pneumothorax, interstitial lung disease, arrhythmia, acute cardiac failure, myocarditis, cerebrovascular accident, death of unknown cause, and acute myeloid leukemia (1 patient each).

Serious adverse reactions occurred in 18% of patients receiving TECENTRIQ. The most frequent serious adverse reactions (>1%) were pneumonia (1.8%), pneumonitis (1.6%), and pyrexia (1.2%).

TECENTRIQ was discontinued due to adverse reactions in 18% of patients; the most common adverse reactions (≥1%) leading to TECENTRIQ discontinuation were pneumonitis (2.2%), hypothyroidism (1.6%), increased aspartate aminotransferase (1.4%), arthralgia (1.0%), and increased alanine aminotransferase (1.0%).

Adverse reactions leading to interruption of TECENTRIQ occurred in 29% of patients; the most common (>1%) were rash (3.0%), hyperthyroidism (2.8%), hypothyroidism (1.6%), increased AST (1.6%), pyrexia (1.6%), increased ALT (1.4%), upper respiratory tract infection (1.4%), headache (1.2%), peripheral neuropathy (1.2%), and pneumonia (1.2%).

Tables 4 and 5 summarize adverse reactions and selected laboratory abnormalities in patients receiving TECENTRIQ in IMpower010.

Table 4: Adverse Reactions Occurring in ≥10% of Patients with Early-Stage NSCLC Receiving TECENTRIQ in IMpower010
Adverse Reaction [Graded per NCI CTCAE v4.0] | TECENTRIQ N = 495 |  | Best Supportive Care N = 495
Adverse Reaction [Graded per NCI CTCAE v4.0] | All Grades (%) | Grades 3–4 (%) | All Grades (%) | Grades 3–4 (%)
Skin and Subcutaneous Tissue
Rash [Includes rash, dermatitis, genital rash, skin exfoliation, rash maculo-papular, rash erythematous, rash papular, lichen planus, eczema asteatotic, dermatitis exfoliative, palmar-plantar erythrodysaesthesia syndrome, dyshidrotic eczema, eczema, drug eruption, rash pruritic, toxic skin eruption, dermatitis acneiform] | 17 | 1.2 | 1.4 | 0
Pruritus | 10 | 0 | 0.6 | 0
Endocrine Disorders
Hypothyroidism [Includes hypothyroidism, autoimmune hypothyroidism, primary hypothyroidism, blood thyroid stimulating hormone increased] | 14 | 0 | 0.6 | 0
Respiratory, Thoracic and Mediastinal
Cough [Productive cough, upper airway cough syndrome, cough] | 16 | 0 | 11 | 0
General
Pyrexia [Includes pyrexia, body temperature increased, hyperthermia] | 14 | 0.8 | 2.2 | 0.2
Fatigue [Includes fatigue, asthenia] | 14 | 0.6 | 5 | 0.2
Nervous System Disorders
Peripheral neuropathy [Includes paraesthesia, neuropathy peripheral, peripheral sensory neuropathy, hypoaesthesia, polyneuropathy, dysaesthesia, neuralgia, axonal neuropathy] | 12 | 0.4 | 7 | 0.2
Musculoskeletal and Connective Tissue
Musculoskeletal pain [Includes myalgia, bone pain, back pain, spinal pain, musculoskeletal chest pain, pain in extremity, neck pain, non-cardiac chest pain, musculoskeletal discomfort, musculoskeletal stiffness, musculoskeletal pain] | 14 | 0.8 | 9 | 0.2
Arthralgia [Includes arthralgia, arthritis] | 11 | 0.6 | 6 | 0

Table 5: Laboratory Abnormalities Worsening from Baseline Occurring in ≥20% of Patients with Early-Stage NSCLC Receiving TECENTRIQ in IMpower010
Laboratory Abnormality [Graded per NCI CTCAE v4.0, except for increased creatinine which only includes patients with creatinine increase based on upper limit of normal definition for Grade 1 events (NCI CTCAE v5.0).] | TECENTRIQ [The denominators used to calculate the rate varied from 78-480 for BSC arm and 483 for TECENTRIQ are for all tests of interest based on the number of patients with a baseline value and at least one post-treatment value.] |  | Best Supportive Care
Laboratory Abnormality [Graded per NCI CTCAE v4.0, except for increased creatinine which only includes patients with creatinine increase based on upper limit of normal definition for Grade 1 events (NCI CTCAE v5.0).] | All Grades (%) | Grades 3–4 (%) | All Grades (%) | Grades 3–4 (%)
Chemistry
Increased aspartate aminotransferase | 34 | 2.5 | 18 | 0
Increased alanine aminotransferase | 30 | 3.3 | 19 | 0.4
Hyperkalemia | 24 | 3.5 | 15 | 2.5
Increased blood creatinine | 31 | 0.2 | 23 | 0.2

Metastatic Chemotherapy-Naïve NSCLC

IMpower110

The safety of TECENTRIQ was evaluated in IMpower110, a multicenter, international, randomized, open-label study in 549 chemotherapy-naïve patients with stage IV NSCLC, including those with EGFR or ALK genomic tumor aberrations. Patients received TECENTRIQ 1200 mg every 3 weeks (n=286) or platinum-based chemotherapy consisting of carboplatin or cisplatin with either pemetrexed or gemcitabine (n=263) until disease progression or unacceptable toxicity [see Clinical Studies (14.1)]. IMpower110 enrolled patients whose tumors express PD-L1 (PD-L1 stained ≥ 1% of tumor cells [TC] or PD-L1 stained tumor-infiltrating immune cells [IC] covering ≥ 1% of the tumor area). The median duration of exposure to TECENTRIQ was 5.3 months (0 to 33 months).

Fatal adverse reactions occurred in 3.8% of patients receiving TECENTRIQ; these included death (reported as unexplained death and death of unknown cause), aspiration, chronic obstructive pulmonary disease, pulmonary embolism, acute myocardial infarction, cardiac arrest, mechanical ileus, sepsis, cerebral infarction, and device occlusion (1 patient each).

Serious adverse reactions occurred in 28% of patients receiving TECENTRIQ. The most frequent serious adverse reactions (>2%) were pneumonia (2.8%), chronic obstructive pulmonary disease (2.1%) and pneumonitis (2.1%).

TECENTRIQ was discontinued due to adverse reactions in 6% of patients; the most common adverse reactions (≥2 patients) leading to TECENTRIQ discontinuation were peripheral neuropathy and pneumonitis.

Adverse reactions leading to interruption of TECENTRIQ occurred in 26% of patients; the most common (>1%) were ALT increased (2.1%), AST increased (2.1%), pneumonitis (2.1%), pyrexia (1.4%), pneumonia (1.4%) and upper respiratory tract infection (1.4%).

Tables 6 and 7 summarize adverse reactions and selected laboratory abnormalities in patients receiving TECENTRIQ in IMpower110.

Table 6: Adverse Reactions Occurring in ≥10% of Patients with NSCLC Receiving TECENTRIQ in IMpower110
Adverse Reaction | TECENTRIQ N = 286 |  | Platinum-Based Chemotherapy N = 263
Adverse Reaction | All Grades (%) | Grades 3–4 (%) | All Grades (%) | Grades 3–4 (%)
Gastrointestinal
Nausea | 14 | 0.3 | 34 | 1.9
Constipation | 12 | 1.0 | 22 | 0.8
Diarrhea | 11 | 0 | 12 | 0.8
General
Fatigue/asthenia | 25 | 1.4 | 34 | 4.2
Pyrexia | 14 | 0 | 9 | 0.4
Metabolism and Nutrition
Decreased appetite | 15 | 0.7 | 19 | 0
Respiratory, Thoracic and Mediastinal
Dyspnea | 14 | 0.7 | 10 | 0
Cough | 12 | 0.3 | 10 | 0
Graded per NCI CTCAE v4.0

Table 7: Laboratory Abnormalities Worsening from Baseline Occurring in ≥20% of Patients Receiving TECENTRIQ in IMpower110
Laboratory Abnormality | TECENTRIQ |  | Platinum-Based Chemotherapy
Laboratory Abnormality | All Grades (%) | Grades 3–4 (%) | All Grades (%) | Grades 3–4 (%)
Hematology
Anemia | 69 | 1.8 | 94 | 20
Lymphopenia | 47 | 9 | 59 | 17
Chemistry
Hypoalbuminemia | 48 | 0.4 | 39 | 2
Increased alkaline phosphatase | 46 | 2.5 | 42 | 1.2
Hyponatremia | 44 | 9 | 36 | 7
Increased ALT | 38 | 3.2 | 32 | 0.8
Increased AST | 36 | 3.2 | 32 | 0.8
Hyperkalemia | 29 | 3.9 | 36 | 2.7
Hypocalcemia | 24 | 1.4 | 24 | 2.7
Increased blood creatinine | 24 | 0.7 | 33 | 1.5
Hypophosphatemia | 23 | 3.6 | 21 | 2
Each test incidence is based on the number of patients who had at least one on-study laboratory measurement available: TECENTRIQ (range: 278-281); platinum-based chemotherapy (range: 256-260). Graded per NCI CTCAE v4.0. Increased blood creatinine only includes patients with test results above the normal range.

IMpower150

The safety of TECENTRIQ with bevacizumab, paclitaxel and carboplatin was evaluated in IMpower150, a multicenter, international, randomized, open-label trial in which 393 chemotherapy-naïve patients with metastatic non-squamous NSCLC received TECENTRIQ 1200 mg with bevacizumab 15 mg/kg, paclitaxel 175 mg/m^2 or 200 mg/m^2, and carboplatin AUC 6 mg/mL/min intravenously every 3 weeks for a maximum of 4 or 6 cycles, followed by TECENTRIQ 1200 mg with bevacizumab 15 mg/kg intravenously every 3 weeks until disease progression or unacceptable toxicity [see Clinical Studies (14.1)]. The median duration of exposure to TECENTRIQ was 8.3 months in patients receiving TECENTRIQ with bevacizumab, paclitaxel, and carboplatin.

Fatal adverse reactions occurred in 6% of patients receiving TECENTRIQ; these included hemoptysis, febrile neutropenia, pulmonary embolism, pulmonary hemorrhage, death, cardiac arrest, cerebrovascular accident, pneumonia, aspiration pneumonia, chronic obstructive pulmonary disease, intracranial hemorrhage, intestinal angina, intestinal ischemia, intestinal obstruction and aortic dissection.

Serious adverse reactions occurred in 44%. The most frequent serious adverse reactions (>2%) were febrile neutropenia, pneumonia, diarrhea, and hemoptysis.

TECENTRIQ was discontinued due to adverse reactions in 15% of patients; the most common adverse reaction leading to discontinuation was pneumonitis (1.8%).

Adverse reactions leading to interruption of TECENTRIQ occurred in 48%; the most common (>1%) were neutropenia, thrombocytopenia, fatigue/asthenia, diarrhea, hypothyroidism, anemia, pneumonia, pyrexia, hyperthyroidism, febrile neutropenia, increased ALT, dyspnea, dehydration and proteinuria.

Tables 8 and 9 summarize adverse reactions and laboratory abnormalities in patients receiving TECENTRIQ with bevacizumab, paclitaxel, and carboplatin in IMpower150.

Table 8: Adverse Reactions Occurring in ≥15% of Patients with NSCLC Receiving TECENTRIQ in IMpower150
Adverse Reaction | TECENTRIQ with Bevacizumab, Paclitaxel, and Carboplatin N = 393 |  | Bevacizumab, Paclitaxel and Carboplatin N = 394
Adverse Reaction | All Grades (%) | Grades 3–4 (%) | All Grades (%) | Grades 3–4 (%)
Nervous System
Neuropathy [Includes neuropathy peripheral, peripheral sensory neuropathy, hypoesthesia, paraesthesia, dysesthesia, polyneuropathy] | 56 | 3 | 47 | 3
Headache | 16 | 0.8 | 13 | 0
General
Fatigue/Asthenia | 50 | 6 | 46 | 6
Pyrexia | 19 | 0.3 | 9 | 0.5
Skin and Subcutaneous Tissue
Alopecia | 48 | 0 | 46 | 0
Rash [Includes rash, rash maculo-papular, drug eruption, eczema, eczema asteatotic, dermatitis, contact dermatitis, rash erythematous, rash macular, pruritic rash, seborrheic dermatitis, dermatitis psoriasiform] | 23 | 2 | 10 | 0.3
Musculoskeletal and Connective Tissue
Myalgia/Pain [Includes pain in extremity, musculoskeletal chest pain, musculoskeletal discomfort, neck pain, back pain, myalgia, and bone pain] | 42 | 3 | 34 | 2
Arthralgia | 26 | 1 | 22 | 1
Gastrointestinal
Nausea | 39 | 4 | 32 | 2
Diarrhea [Includes diarrhea, gastroenteritis, colitis, enterocolitis] | 33 | 6 | 25 | 0.5
Constipation | 30 | 0.3 | 23 | 0.3
Vomiting | 19 | 2 | 18 | 1
Metabolism and Nutrition
Decreased appetite | 29 | 4 | 21 | 0.8
Vascular
Hypertension | 25 | 9 | 22 | 8
Respiratory
Cough | 20 | 0.8 | 19 | 0.3
Epistaxis | 17 | 1 | 22 | 0.3
Renal
Proteinuria [Data based on Preferred Terms since laboratory data for proteinuria were not systematically collected] | 16 | 3 | 15 | 3
Graded per NCI CTCAE v4.0

Table 9: Laboratory Abnormalities Worsening from Baseline Occurring in ≥20% of Patients with NSCLC Receiving TECENTRIQ in IMpower150
Laboratory Abnormality | TECENTRIQ with Bevacizumab, Paclitaxel, and Carboplatin |  | Bevacizumab, Paclitaxel and Carboplatin
Laboratory Abnormality | All Grades (%) | Grades 3–4 (%) | All Grades (%) | Grades 3–4 (%)
Hematology
Anemia | 83 | 10 | 83 | 9
Neutropenia | 52 | 31 | 45 | 26
Lymphopenia | 48 | 17 | 38 | 13
Chemistry
Hyperglycemia | 61 | 0 | 60 | 0
Increased BUN | 52 | NA [NA = Not applicable. NCI CTCAE does not provide a Grades 3-4 definition for these laboratory abnormalities] | 44 | NA
Hypomagnesemia | 42 | 2 | 36 | 1
Hypoalbuminemia | 40 | 3 | 31 | 2
Increased AST | 40 | 4 | 28 | 0.8
Hyponatremia | 38 | 10 | 36 | 9
Increased Alkaline Phosphatase | 37 | 2 | 32 | 1
Increased ALT | 37 | 6 | 28 | 0.5
Increased TSH | 30 | NA | 20 | NA
Hyperkalemia | 28 | 3 | 25 | 2
Increased Creatinine | 28 | 1 | 19 | 2
Hypocalcemia | 26 | 3 | 21 | 3
Hypophosphatemia | 25 | 4 | 18 | 4
Hypokalemia | 23 | 7 | 14 | 4
Hyperphosphatemia | 25 | NA | 19 | NA
Each test incidence is based on the number of patients who had both baseline and at least one on-study laboratory measurement available: TECENTRIQ with bevacizumab, paclitaxel, and carboplatin range: 337-380); bevacizumab, paclitaxel, and carboplatin (range: 337-382). Graded per NCI CTCAE v4.0

IMpower130

The safety of TECENTRIQ with paclitaxel protein-bound and carboplatin was evaluated in IMpower130, a multicenter, international, randomized, open-label trial in which 473 chemotherapy-naïve patients with metastatic non-squamous NSCLC received TECENTRIQ 1200 mg and carboplatin AUC 6 mg/mL/min intravenously on Day 1 and paclitaxel protein-bound 100 mg/m^2 intravenously on Day 1, 8, and 15 of each 21-day cycle for a maximum of 4 or 6 cycles, followed by TECENTRIQ 1200 mg intravenously every 3 weeks until disease progression or unacceptable toxicity [see Clinical Studies (14.1)]. Among patients receiving TECENTRIQ, 55% were exposed for 6 months or longer and 3.5% were exposed for greater than one year.

Fatal adverse reactions occurred in 5.3% of patients receiving TECENTRIQ; these included pneumonia (1.1%), pulmonary embolism (0.8%), myocardial infarction (0.6%), cardiac arrest (0.4%), pneumonitis (0.4%) and sepsis, septic shock, staphylococcal sepsis, aspiration, respiratory distress, cardiorespiratory arrest, ventricular tachycardia, death (not otherwise specified), and hepatic cirrhosis (0.2% each).

Serious adverse reactions occurred in 51% of patients receiving TECENTRIQ. The most frequent serious adverse reactions (≥2%) were pneumonia (6%), diarrhea (3%), lung infection (3%), pulmonary embolism (3%), chronic obstructive pulmonary disease exacerbation (2.5%), dyspnea (2.3%), and febrile neutropenia (1.9%).

TECENTRIQ was discontinued due to adverse reactions in 13% of patients; the most common adverse reactions leading to discontinuation were pneumonia (0.8%), pulmonary embolism (0.8%), fatigue (0.6%), dyspnea (0.6%), pneumonitis (0.6%), neutropenia (0.4%), nausea (0.4%), renal failure (0.4%), cardiac arrest (0.4%), and septic shock (0.4%).

Adverse reactions leading to interruption of TECENTRIQ occurred in 62% of patients; the most common (>1%) were neutropenia, thrombocytopenia, anemia, diarrhea, fatigue/asthenia, pneumonia, dyspnea, pneumonitis, pyrexia, nausea, acute kidney injury, vomiting, pulmonary embolism, arthralgia, infusion-related reaction, abdominal pain, chronic obstructive pulmonary disease exacerbation, dehydration, and hypokalemia.

Tables 10 and 11 summarize adverse reactions and laboratory abnormalities in patients receiving TECENTRIQ with paclitaxel protein-bound and carboplatin in IMpower130.

Table 10: Adverse Reactions Occurring in ≥20% of Patients with NSCLC Receiving TECENTRIQ in IMpower130
Adverse Reaction | TECENTRIQ with Paclitaxel Protein-Bound and Carboplatin N = 473 |  | Paclitaxel Protein-Bound and Carboplatin N = 232
Adverse Reaction | All Grades (%) | Grades 3–4 (%) | All Grades (%) | Grades 3–4 (%)
General
Fatigue/Asthenia | 61 | 11 | 60 | 8
Gastrointestinal
Nausea | 50 | 3.4 | 46 | 2.2
Diarrhea [Includes diarrhea, colitis, and gastroenteritis] | 43 | 6 | 32 | 6
Constipation | 36 | 1.1 | 31 | 0
Vomiting | 27 | 2.7 | 19 | 2.2
Musculoskeletal and Connective Tissue
Myalgia/Pain [Includes back pain, pain in extremity, myalgia, musculoskeletal chest pain, bone pain, neck pain and musculoskeletal discomfort] | 38 | 3 | 22 | 0.4
Nervous System
Neuropathy [Includes neuropathy peripheral, peripheral sensory neuropathy, hypoesthesia, paresthesia, dysesthesia, polyneuropathy] | 33 | 2.5 | 28 | 2.2
Respiratory, Thoracic and Mediastinal
Dyspnea [Includes dyspnea, dyspnea exertional and wheezing] | 32 | 4.9 | 25 | 1.3
Cough | 27 | 0.6 | 17 | 0
Skin and Subcutaneous Tissue
Alopecia | 32 | 0 | 27 | 0
Rash [Includes rash, rash maculo-papular, eczema, rash pruritic, rash erythematous, dermatitis, dermatitis contact, drug eruption, seborrheic dermatitis and rash macular.] | 20 | 0.6 | 11 | 0.9
Metabolism and Nutrition
Decreased appetite | 30 | 2.1 | 26 | 2.2
Graded per NCI CTCAE v4.0

Table 11: Laboratory Abnormalities Worsening from Baseline Occurring in ≥20% of Patients Receiving TECENTRIQ in IMpower130
Laboratory Abnormality | TECENTRIQ with Paclitaxel Protein-Bound and Carboplatin N = 473 |  | Paclitaxel Protein-Bound and Carboplatin N = 232
Laboratory Abnormality | All Grades (%) | Grades 3–4 (%) | All Grades (%) | Grades 3–4 (%)
Hematology
Anemia | 92 | 33 | 87 | 25
Neutropenia | 75 | 50 | 67 | 39
Thrombocytopenia | 73 | 19 | 59 | 13
Lymphopenia | 71 | 23 | 61 | 16
Chemistry
Hyperglycemia | 75 | 8 | 66 | 8
Hypomagnesemia | 50 | 3.4 | 42 | 3.2
Hyponatremia | 37 | 9 | 28 | 7
Hypoalbuminemia | 35 | 1.3 | 31 | 0
Increased ALT | 31 | 2.8 | 24 | 3.9
Hypocalcemia | 31 | 2.6 | 27 | 1.8
Hypophosphatemia | 29 | 6 | 20 | 3.2
Increased AST | 28 | 2.2 | 24 | 1.8
Increased TSH | 26 | NA [NA = Not applicable. NCI CTCAE does not provide a Grades 3-4 definition for these laboratory abnormalities] | 5 | NA
Hypokalemia | 26 | 6 | 24 | 4.4
Increased Alkaline Phosphatase | 25 | 2.6 | 22 | 1.3
Increased Blood Creatinine | 23 | 2.8 | 16 | 0.4
Hyperphosphatemia | 21 | NA | 13 | NA
Each test incidence is based on the number of patients who had both baseline and at least one on-study laboratory measurement available: TECENTRIQ with paclitaxel protein-bound and carboplatin (range: 423 - 467); paclitaxel protein-bound and carboplatin (range: 218 - 229). Graded per NCI CTCAE v4.0.

Previously Treated Metastatic NSCLC

OAK

The safety of TECENTRIQ was evaluated in OAK, a multicenter, international, randomized, open-label trial in patients with metastatic NSCLC who progressed during or following a platinum-containing regimen, regardless of PD-L1 expression [see Clinical Studies (14.1)]. A total of 609 patients received TECENTRIQ 1200 mg intravenously every 3 weeks until unacceptable toxicity, radiographic progression, or clinical progression or docetaxel (n=578) 75 mg/m^2 intravenously every 3 weeks until unacceptable toxicity or disease progression. The study excluded patients with active or prior autoimmune disease or with medical conditions that required systemic corticosteroids. The median duration of exposure was 3.4 months (0 to 26 months) in TECENTRIQ-treated patients and 2.1 months (0 to 23 months) in docetaxel-treated patients.

The study population characteristics were: median age of 63 years (25 to 85 years), 46% age 65 years or older, 62% male, 71% White, 20% Asian, 68% former smoker, 16% current smoker, and 63% had Eastern Cooperative Oncology Group (ECOG) performance status of 1.

Fatal adverse reactions occurred in 1.6% of patients; these included pneumonia, sepsis, septic shock, dyspnea, pulmonary hemorrhage, sudden death, myocardial ischemia or renal failure.

Serious adverse reactions occurred in 33.5% of patients. The most frequent serious adverse reactions (>1%) were pneumonia, sepsis, dyspnea, pleural effusion, pulmonary embolism, pyrexia and respiratory tract infection.

TECENTRIQ was discontinued due to adverse reactions in 8% of patients. The most common adverse reactions leading to TECENTRIQ discontinuation were fatigue, infections and dyspnea. Adverse reactions leading to interruption of TECENTRIQ occurred in 25% of patients; the most common (>1%) were pneumonia, liver function test abnormality, dyspnea, fatigue, pyrexia, and back pain.

Tables 12 and 13 summarize adverse reactions and laboratory abnormalities, respectively, in OAK.

Table 12: Adverse Reactions Occurring in ≥10% of Patients with NSCLC Receiving TECENTRIQ in OAK
Adverse Reaction | TECENTRIQ N = 609 |  | Docetaxel N = 578
Adverse Reaction | All Grades (%) | Grades 3–4 (%) | All Grades (%) | Grades 3–4 (%)
General
Fatigue/Asthenia [Includes fatigue and asthenia] | 44 | 4 | 53 | 6
Pyrexia | 18 | <1 | 13 | <1
Respiratory
Cough [Includes cough and exertional cough] | 26 | <1 | 21 | <1
Dyspnea | 22 | 2.8 | 21 | 2.6
Metabolism and Nutrition
Decreased appetite | 23 | <1 | 24 | 1.6
Musculoskeletal
Myalgia/Pain [Includes musculoskeletal pain, musculoskeletal stiffness, musculoskeletal chest pain, myalgia] | 20 | 1.3 | 20 | <1
Arthralgia | 12 | 0.5 | 10 | 0.2
Gastrointestinal
Nausea | 18 | <1 | 23 | <1
Constipation | 18 | <1 | 14 | <1
Diarrhea | 16 | <1 | 24 | 2
Skin
Rash [Includes rash, erythematous rash, generalized rash, maculopapular rash, papular rash, pruritic rash, pustular rash, pemphigoid] | 12 | <1 | 10 | 0
Graded per NCI CTCAE v4.0

Table 13: Laboratory Abnormalities Worsening from Baseline Occurring in ≥20% of Patients with NSCLC Receiving TECENTRIQ in OAK
Laboratory Abnormality | TECENTRIQ |  | Docetaxel
Laboratory Abnormality | All Grades (%) | Grades 3–4 (%) | All Grades (%) | Grades 3–4 (%)
Hematology
Anemia | 67 | 3 | 82 | 7
Lymphocytopenia | 49 | 14 | 60 | 21
Chemistry
Hypoalbuminemia | 48 | 4 | 50 | 3
Hyponatremia | 42 | 7 | 31 | 6
Increased Alkaline Phosphatase | 39 | 2 | 25 | 1
Increased AST | 31 | 3 | 16 | 0.5
Increased ALT | 27 | 3 | 14 | 0.5
Hypophosphatemia | 27 | 5 | 23 | 4
Hypomagnesemia | 26 | 1 | 21 | 1
Increased Creatinine | 23 | 2 | 16 | 1
Each test incidence is based on the number of patients who had both baseline and at least one on-study laboratory measurement available: TECENTRIQ (range: 546–585) and docetaxel (range: 532–560). Graded according to NCI CTCAE version 4.0

Small Cell Lung Cancer (SCLC)

IMpower133

The safety of TECENTRIQ with carboplatin and etoposide was evaluated in IMpower133, a randomized, multicenter, double-blind, placebo-controlled trial in which 198 patients with ES-SCLC received TECENTRIQ 1200 mg and carboplatin AUC 5 mg/mL/min on Day 1 and etoposide 100 mg/m^2 intravenously on Days 1, 2 and 3 of each 21-day cycle for a maximum of 4 cycles, followed by TECENTRIQ 1200 mg every 3 weeks until disease progression or unacceptable toxicity [see Clinical Studies (14.2)]. Among 198 patients receiving TECENTRIQ, 32% were exposed for 6 months or longer and 12% were exposed for 12 months or longer.

Fatal adverse reactions occurred in 2% of patients receiving TECENTRIQ. These included pneumonia, respiratory failure, neutropenia, and death (1 patient each).

Serious adverse reactions occurred in 37% of patients receiving TECENTRIQ. Serious adverse reactions in >2% were pneumonia (4.5%), neutropenia (3.5%), febrile neutropenia (2.5%), and thrombocytopenia (2.5%).

TECENTRIQ was discontinued due to adverse reactions in 11% of patients. The most frequent adverse reaction requiring permanent discontinuation in >2% of patients was infusion-related reactions (2.5%).

Adverse reactions leading to interruption of TECENTRIQ occurred in 59% of patients; the most common (>1%) were neutropenia (22%), anemia (9%), leukopenia (7%), thrombocytopenia (5%), fatigue (4.0%), infusion-related reaction (3.5%), pneumonia (2.0%), febrile neutropenia (1.5%), increased ALT (1.5%), and nausea (1.5%).

Tables 14 and 15 summarize adverse reactions and laboratory abnormalities, respectively, in patients who received TECENTRIQ with carboplatin and etoposide in IMpower133.

Table 14: Adverse Reactions Occurring in ≥20% of Patients with SCLC Receiving TECENTRIQ in IMpower133
Adverse Reaction | TECENTRIQ with Carboplatin and Etoposide N = 198 |  | Placebo with Carboplatin and Etoposide N = 196
Adverse Reaction | All Grades (%) | Grades 3–4 (%) | All Grades (%) | Grades 3–4 (%)
General
Fatigue/asthenia | 39 | 5 | 33 | 3
Gastrointestinal
Nausea | 38 | 1 | 33 | 1
Constipation | 26 | 1 | 30 | 1
Vomiting | 20 | 2 | 17 | 3
Skin and Subcutaneous Tissue
Alopecia | 37 | 0 | 35 | 0
Metabolism and Nutrition
Decreased appetite | 27 | 1 | 18 | 0
Graded per NCI CTCAE v4.0

Table 15: Laboratory Abnormalities Worsening from Baseline Occurring in ≥20% of Patients with SCLC Receiving TECENTRIQ in IMpower133
Laboratory Abnormality | TECENTRIQ with Carboplatin and Etoposide |  | Placebo with Carboplatin and Etoposide
Laboratory Abnormality | All Grades (%) | Grades 3–4 (%) | All Grades (%) | Grades 3–4 (%)
Hematology
Anemia | 94 | 17 | 93 | 19
Neutropenia | 73 | 45 | 76 | 48
Thrombocytopenia | 58 | 20 | 53 | 17
Lymphopenia | 46 | 14 | 38 | 11
Chemistry
Hyperglycemia | 67 | 10 | 65 | 8
Increased Alkaline Phosphatase | 38 | 1 | 35 | 2
Hyponatremia | 34 | 15 | 33 | 11
Hypoalbuminemia | 32 | 1 | 30 | 0
Decreased TSH [TSH = thyroid-stimulating hormone. NCI CTCAE v4.0 does not include these laboratories.] | 28 | NA [NA = Not applicable.] | 15 | NA
Hypomagnesemia | 31 | 5 | 35 | 6
Hypocalcemia | 26 | 3 | 28 | 5
Increased ALT | 26 | 3 | 31 | 1
Increased AST | 22 | 1 | 21 | 2
Increased Blood Creatinine | 22 | 4 | 15 | 1
Hyperphosphatemia | 21 | NA | 23 | NA
Increased TSH | 21 | NA | 7 | NA
Each test incidence is based on the number of patients who had both baseline and at least one on-study laboratory measurement available: TECENTRIQ (range: 181-193); Placebo (range: 181-196). Graded per NCI CTCAE v4.0

IMforte

The safety of TECENTRIQ in combination with lurbinectedin was evaluated in IMforte [see Clinical Studies (14.2)]. Patients received TECENTRIQ 1200 mg IV and lurbinectedin 3.2 mg/m^2 IV, on Day 1 of each 21-day cycle until disease progression or unacceptable toxicity. Primary prophylaxis of G-CSF was administered to 84% of patients. Among 242 patients receiving TECENTRIQ with lurbinectedin, the median duration of exposure to TECENTRIQ was 4.2 months, with 34% of patients exposed for 6 months or longer and 8% of patients exposed for 12 months or longer.

Serious adverse reactions occurred in 31% of patients receiving TECENTRIQ with lurbinectedin. Serious adverse reactions in >2% of patients were pneumonia (2.5%), respiratory tract infection (2.1%), dyspnea (2.1%), and decreased platelet count (2.1%). Fatal adverse reactions occurred in 5% of patients receiving TECENTRIQ with lurbinectedin including pneumonia (3 patients), sepsis (3 patients), cardio-respiratory arrest (2 patients), myocardial infarction (2 patients) and febrile neutropenia (1 patient).

Permanent discontinuation of TECENTRIQ due to an adverse reaction occurred in 2.5% of patients. The adverse reactions requiring permanent discontinuation in ≥ 1% of patients who received TECENTRIQ were immune-mediated nephritis, peripheral neuropathy, nephropathy, pneumonitis, anemia, neutropenia, and thrombocytopenia.

Dosage interruptions of TECENTRIQ due to an adverse reaction occurred in 29% of patients. Adverse reactions which required dosage interruption in ≥ 2% of patients included anemia, fatigue, decreased neutrophil count, pneumonitis, and decreased platelet count.

Tables 16 and 17 summarize adverse reactions and laboratory abnormalities, respectively, in patients who received TECENTRIQ with lurbinectedin in IMforte.

Table 16: Adverse Reactions (≥10%) in Patients with ES-SCLC Who Received TECENTRIQ with Lurbinectedin in IMforte
Adverse Reaction | TECENTRIQ with Lurbinectedin N = 242 |  | TECENTRIQ N = 240
Adverse Reaction | All Grades (%) | Grades 3 or 4 (%) | All Grades (%) | Grades 3 or 4 (%)
Gastrointestinal
Nausea | 36 | 3 | 4 | 1
Diarrhea [Includes diarrhea and colitis.] | 15 | 0 | 8 | 0
Vomiting | 14 | 1 | 3 | 0
Constipation | 12 | 0 | 6 | 1
General disorders and administration site conditions
Fatigue [Includes fatigue and asthenia.] | 32 | 5 | 13 | 2
Musculoskeletal and connective tissue disorders
Musculoskeletal Pain [Includes arthralgia, arthritis, back pain, bone pain, musculoskeletal chest pain, musculoskeletal discomfort, musculoskeletal pain, myalgia, neck pain, non-cardiac chest pain, and pain in extremity.] | 19 | 2 | 16 | 1
Metabolism and Nutrition
Decreased appetite | 17 | 0 | 7 | 0
Respiratory, thoracic and mediastinal disorders
Cough [Includes cough, productive cough, and upper-airway cough syndrome.] | 12 | 0 | 8 | 0
Dyspnea [Includes dyspnea and dyspnea exertional.] | 11 | 2 | 10 | 2
Graded per NCI CTCAE v5.0

Clinically relevant adverse reactions in < 10% of patients who received TECENTRIQ in combination with lurbinectedin included pneumonia, phlebitis, extravasation resulting in skin necrosis, hypersensitivity and increased creatine phosphokinase.

Table 17: Select Laboratory Abnormalities (≥20%) That Worsened from Baseline in Patients with ES-SCLC Who Received TECENTRIQ in Combination with Lurbinectedin in IMforte
Laboratory Abnormality | TECENTRIQ with Lurbinectedin N = 242 |  | TECENTRIQ N = 240
Laboratory Abnormality | All Grades (%) | Grades 3 or 4 (%) | All Grades (%) | Grades 3 or 4 (%)
Hematology
Lymphopenia | 55 | 17 | 31 | 11
Thrombocytopenia | 54 | 15 | 15 | 3
Anemia | 51 | 13 | 12 | 3
Neutropenia | 36 | 18 | 7 | 4
Chemistry
Increased alkaline phosphatase | 29 | 1 | 14 | 0
Decreased sodium | 27 | 4 | 30 | 5
Increased ALT | 25 | 3 | 18 | 2
Increased AST | 24 | 3 | 22 | 1
Decreased calcium | 24 | 3 | 8 | 1
Increased creatinine | 21 | 3 | 14 | 0
Graded per NCI CTCAE v5.0

Hepatocellular Carcinoma (HCC)

IMbrave150

The safety of TECENTRIQ in combination with bevacizumab was evaluated in IMbrave150, a multicenter, international, randomized, open-label trial in patients with locally advanced or metastatic or unresectable hepatocellular carcinoma who have not received prior systemic treatment [see Clinical Studies (14.3)]. Patients received 1,200 mg of TECENTRIQ intravenously followed by 15 mg/kg bevacizumab (n=329) every 3 weeks, or 400 mg of sorafenib (n=156) given orally twice daily, until disease progression or unacceptable toxicity. The median duration of exposure to TECENTRIQ was 7.4 months (range: 0-16 months) and to bevacizumab was 6.9 months (range: 0-16 months).

Fatal adverse reactions occurred in 4.6% of patients in the TECENTRIQ and bevacizumab arm. The most common adverse reactions leading to death were gastrointestinal and esophageal varices hemorrhage (1.2%) and infections (1.2%).

Serious adverse reactions occurred in 38% of patients in the TECENTRIQ and bevacizumab arm. The most frequent serious adverse reactions (≥ 2%) were gastrointestinal hemorrhage (7%), infections (6%), and pyrexia (2.1%).

Adverse reactions leading to discontinuation of TECENTRIQ occurred in 9% of patients in the TECENTRIQ and bevacizumab arm. The most common adverse reactions leading to TECENTRIQ discontinuation were hemorrhages (1.2%), including gastrointestinal, subarachnoid, and pulmonary hemorrhages; increased transaminases or bilirubin (1.2%); infusion-related reaction/cytokine release syndrome (0.9%); and autoimmune hepatitis (0.6%).

Adverse reactions leading to interruption of TECENTRIQ occurred in 41% of patients in the TECENTRIQ and bevacizumab arm; the most common (≥ 2%) were liver function laboratory abnormalities including increased transaminases, bilirubin, or alkaline phosphatase (8%); infections (6%); gastrointestinal hemorrhages (3.6%); thrombocytopenia/decreased platelet count (3.6%); hyperthyroidism (2.7%); and pyrexia (2.1%).

Immune-related adverse reactions requiring systemic corticosteroid therapy occurred in 12% of patients in the TECENTRIQ and bevacizumab arm.

Tables 18 and 19 summarize adverse reactions and laboratory abnormalities, respectively, in patients who received TECENTRIQ and bevacizumab in IMbrave150.

Table 18: Adverse Reactions Occurring in ≥10% of Patients with HCC Receiving TECENTRIQ in IMbrave150
Adverse Reaction | TECENTRIQ in combination with Bevacizumab (n = 329) |  | Sorafenib (n=156)
Adverse Reaction | All Grades [Graded per NCI CTCAE v4.0] (%) | Grades 3–4 (%) | All Grades (%) | Grades 3–4 (%)
Vascular Disorders
Hypertension | 30 | 15 | 24 | 12
General Disorders and Administration Site Conditions
Fatigue/asthenia [Includes fatigue and asthenia] | 26 | 2 | 32 | 6
Pyrexia | 18 | 0 | 10 | 0
Renal and Urinary Disorders
Proteinuria | 20 | 3 | 7 | 0.6
Investigations
Weight Decreased | 11 | 0 | 10 | 0
Skin and Subcutaneous Tissue Disorders
Pruritus | 19 | 0 | 10 | 0
Rash | 12 | 0 | 17 | 2.6
Gastrointestinal Disorders
Diarrhea | 19 | 1.8 | 49 | 5
Constipation | 13 | 0 | 14 | 0
Abdominal Pain | 12 | 0 | 17 | 0
Nausea | 12 | 0 | 16 | 0
Vomiting | 10 | 0 | 8 | 0
Metabolism and Nutrition Disorders
Decreased Appetite | 18 | 1.2 | 24 | 3.8
Respiratory, Thoracic and Mediastinal Disorders
Cough | 12 | 0 | 10 | 0
Epistaxis | 10 | 0 | 4.5 | 0
Injury, Poisoning and Procedural Complications
Infusion-Related Reaction | 11 | 2.4 | 0 | 0

Table 19: Laboratory Abnormalities Worsening from Baseline Occurring in ≥20% of Patients with HCC Receiving TECENTRIQ in IMbrave150
Laboratory Abnormality | TECENTRIQ in combination with Bevacizumab (n = 329) |  | Sorafenib (n=156)
Laboratory Abnormality | All Grades [Graded per NCI CTCAE v4.0] (%) | Grades 3–4 (%) | All Grades (%) | Grades 3–4 (%)
Chemistry
Increased AST | 86 | 16 | 90 | 16
Increased Alkaline Phosphatase | 70 | 4 | 76 | 4.6
Increased ALT | 62 | 8 | 70 | 4.6
Decreased Albumin | 60 | 1.5 | 54 | 0.7
Decreased Sodium | 54 | 13 | 49 | 9
Increased Glucose | 48 | 9 | 43 | 4.6
Decreased Calcium | 30 | 0.3 | 35 | 1.3
Decreased Phosphorus | 26 | 4.7 | 58 | 16
Increased Potassium | 23 | 1.9 | 16 | 2
Hypomagnesemia | 22 | 0 | 22 | 0
Hematology
Decreased Platelet | 68 | 7 | 63 | 4.6
Decreased Lymphocytes | 62 | 13 | 58 | 11
Decreased Hemoglobin | 58 | 3.1 | 62 | 3.9
Increased Bilirubin | 57 | 8 | 59 | 14
Decreased Leukocyte | 32 | 3.4 | 29 | 1.3
Decreased Neutrophil | 23 | 2.3 | 16 | 1.1
Each test incidence is based on the number of patients who had both baseline and at least one on-study laboratory measurement available: TECENTRIQ plus bevacizumab (222-323) and sorafenib (90-153)

Melanoma

IMspire150

The safety of TECENTRIQ, administered with cobimetinib and vemurafenib was evaluated in IMspire150, a double-blind, randomized (1:1), placebo-controlled study conducted in patients with previously untreated BRAF V600 mutation-positive metastatic or unresectable melanoma [see Clinical Studies (14.4)]. Patients received TECENTRIQ with cobimetinib and vemurafenib (N=230) or placebo with cobimetinib and vemurafenib (n=281).

Among the 230 patients who received TECENTRIQ administered with cobimetinib and vemurafenib, the median duration of exposure to TECENTRIQ was 9.2 months (range: 0-30 months) to cobimetinib was 10.0 months (range: 1-31 months) and to vemurafenib was 9.8 months (range: 1-31 months).

Fatal adverse reactions occurred in 3% of patients in the TECENTRIQ plus cobimetinib and vemurafenib arm. Adverse reactions leading to death were hepatic failure, fulminant hepatitis, sepsis, septic shock, pneumonia, and cardiac arrest.

Serious adverse reactions occurred in 45% of patients in the TECENTRIQ plus cobimetinib and vemurafenib arm. The most frequent (≥ 2%) serious adverse reactions were hepatotoxicity (7%), pyrexia (6%), pneumonia (4.3%), malignant neoplasms (2.2%), and acute kidney injury (2.2%).

Adverse reactions leading to discontinuation of TECENTRIQ occurred in 21% of patients in the TECENTRIQ plus cobimetinib and vemurafenib arm. The most frequent (≥ 2%) adverse reactions leading to TECENTRIQ discontinuation were increased ALT (2.2%) and pneumonitis (2.6%).

Adverse reactions leading to interruption of TECENTRIQ occurred in 68% of patients in the TECENTRIQ plus cobimetinib and vemurafenib arm. The most frequent (≥ 2%) adverse reactions leading to TECENTRIQ interruption were pyrexia (14%), increased ALT (13%), hyperthyroidism (10%), increased AST (10%), increased lipase (9%), increased amylase (7%), pneumonitis (5%), increased CPK (4.3%), diarrhea (3.5%), pneumonia (3.5%), asthenia (3%), rash (3%), influenza (3%), arthralgia (2.6%), fatigue (2.2%), dyspnea (2.2%), cough (2.2%), peripheral edema (2.2%), uveitis (2.2%), bronchitis (2.2%), hypothyroidism (2.2%), and respiratory tract infection (2.2%).

Tables 20 and 21 summarize the incidence of adverse reactions and laboratory abnormalities in Study IMspire150.

Table 20: Adverse Reactions Occurring in ≥10% of Patients on the TECENTRIQ plus Cobimetinib and Vemurafenib Arm or the Placebo plus Cobimetinib and Vemurafenib Arm and at a Higher Incidence (Between Arm Difference of ≥ 5% All Grades or ≥ 2% Grades 3-4 TECENTRIQ in IMspire150)
Adverse Reaction | TECENTRIQ in combination with Cobimetinib and Vemurafenib (n=230) |  | Placebo with Cobimetinib and Vemurafenib (n=281)
Adverse Reaction | All Grades (%) | Grade 3–4 (%) | All Grades (%) | Grade 3–4 (%)
Skin and Subcutaneous Tissue Disorders
Rash [Includes rash, rash maculo-papular, dermatitis acneiform, rash macular, rash erythematous, eczema, skin exfoliation, rash papular, rash pustular, palmar-plantar erythrodysesthesia syndrome, dermatitis, dermatitis contact, erythema multiforme, rash pruritic, drug eruption, nodular rash, dermatitis allergic, exfoliative rash, dermatitis exfoliative generalized and rash morbilliform] | 75 | 27 | 72 | 23
Pruritus | 26 | <1 | 17 | <1
Photosensitivity reaction | 21 | <1 | 25 | 3.2
General Disorders and Administration Site Conditions
Fatigue [Includes fatigue, asthenia and malaise] | 51 | 3 | 45 | 1.8
Pyrexia [Includes pyrexia and hyperpyrexia] | 49 | 1.7 | 35 | 2.1
Edema [Includes edema peripheral, lymphoedema, edema, face edema, eyelid edema, periorbital edema, lip edema and generalized edema] | 26 | <1 | 21 | 0
Gastrointestinal Disorders
Hepatotoxicity [Includes alanine aminotransferase increased, aspartate aminotransferase increased, blood bilirubin increased, transaminases increased, hepatitis, hepatic enzyme increased, hepatotoxicity, hypertransaminasemia, bilirubin conjugated increased, hepatocellular injury, hyperbilirubinemia, liver function test increased, hepatic failure, hepatitis fulminant and liver function test abnormal] | 50 | 21 | 36 | 13
Nausea | 30 | <1 | 32 | 2.5
Stomatitis [Includes stomatitis, mucosal inflammation, aphthous ulcer, mouth ulceration, cheilitis and glossitis] | 23 | 1.3 | 15 | <1
Musculoskeletal and Connective Tissue Disorders
Musculoskeletal pain [Includes arthralgia, myalgia, pain in extremity, back pain, musculoskeletal pain, arthritis, neck pain, musculoskeletal chest pain, musculoskeletal stiffness, bone pain, spinal pain, immune-mediated arthritis, joint stiffness and non-cardiac chest pain] | 62 | 4.3 | 48 | 3.2
Endocrine Disorders
Hypothyroidism [Includes hypothyroidism and blood thyroid stimulating hormone increased] | 22 | 0 | 10 | 0
Hyperthyroidism | 18 | <1 | 8 | 0
Injury, Poisoning and Procedural Complications
Infusion-related reaction [Includes infusion related reaction and hypersensitivity] | 10 | 2.6 | 8 | <1
Respiratory, Thoracic and Mediastinal Disorders
Pneumonitis [Includes pneumonitis and interstitial lung disease] | 12 | 1.3 | 6 | <1
Vascular Disorders
Hypertension [Includes hypertension, blood pressure increased, hypertensive crisis] | 17 | 10 | 18 | 7

Clinically important adverse reactions in < 10% of patients who received TECENTRIQ plus cobimetinib and vemurafenib were:

Cardiac Disorders: Arrhythmias, ejection fraction decreased, electrocardiogram QT prolonged

Eye Disorders: Uveitis

Gastrointestinal disorders: Pancreatitis

Infections and infestations: Pneumonia, urinary tract infection

Metabolism and nutrition disorders: Hyperglycemia

Nervous system Disorders: Dizziness, dysgeusia, syncope

Respiratory, thoracic and mediastinal disorders: Dyspnea, oropharyngeal pain

Skin and Subcutaneous Tissue Disorders: Vitiligo

Table 21: Laboratory Abnormalities Worsening from Baseline Occurring in ≥ 20% of Patients Receiving TECENTRIQ Plus Cobimetinib and Vemurafenib Arm or the Placebo Plus Cobimetinib and Vemurafenib Arm and at a Higher Incidence (Between Arm Difference of ≥ 5% All Grades or ≥ 2% Grades 3-4) in IMspire150
Laboratory Abnormality | TECENTRIQ in combination with Cobimetinib and Vemurafenib (n=230) |  | Placebo with Cobimetinib and Vemurafenib (n=281)
Laboratory Abnormality | All Grades (%) | Grade 3–4 (%) | All Grades (%) | Grade 3–4 (%)
Hematology
Decreased Lymphocytes | 80 | 24 | 72 | 17
Decreased Hemoglobin | 77 | 2.6 | 72 | 2.2
Decreased Platelet | 34 | 1.3 | 24 | 0.4
Decreased Neutrophils | 26 | 2.2 | 19 | 1.5
Chemistry
Increased Creatine Kinase | 88 | 22 | 81 | 18
Increased AST | 80 | 13 | 68 | 6
Increased ALT | 79 | 18 | 62 | 12
Increased Triacylglycerol Lipase | 75 | 46 | 62 | 35
Increased Alkaline Phosphatase | 73 | 6 | 63 | 2.9
Decreased Phosphorus | 67 | 22 | 64 | 14
Increased Amylase | 51 | 13 | 45 | 13
Increased Blood Urea Nitrogen | 47 | NA [NA= Not applicable. NCI CTCAE v4.0 does not include these laboratories.] | 37 | NA
Decreased Albumin | 43 | 0.9 | 34 | 1.5
Increased Bilirubin | 42 | 3.1 | 33 | 0.7
Decreased Calcium | 41 | 1.3 | 28 | 0
Decreased Sodium | 40 | 5 | 34 | 7
Decreased Thyroid-Stimulating Hormone | 38 | NA | 23 | NA
Increased Thyroid-Stimulating Hormone [Increased Thyroid Stimulating Hormone has a difference <5% (All Grades) between arms and is included for clinical completeness.] | 37 | NA | 33 | NA
Decreased Potassium | 36 | 5 | 22 | 4.3
Increased Triiodothyronine | 33 | NA | 18 | NA
Increased Free Thyroxine | 32 | NA | 21 | NA
Decreased Total Triiodothyronine | 32 | NA | 8 | NA
Increased Potassium | 29 | 1.3 | 19 | 1.4
Decreased Triiodothyronine | 27 | NA | 21 | NA
Increased Sodium | 20 | 0 | 13 | 0.4
Graded per NCI CTCAE v4.0.
Each test incidence is based on the number of patients who had both baseline and at least one on-study laboratory measurement available: TECENTRIQ plus cobimetinib and vemurafenib (28-277), placebo plus cobimetinib and vemurafenib arm (25-230).

Unresectable or Metastatic Alveolar Soft Part Sarcoma (ASPS)

ML39345 Study

The safety of TECENTRIQ was evaluated in 47 adult and 2 pediatric patients enrolled in Study ML39345 [see Clinical Studies (14.5)]. Adult patients received TECENTRIQ 1200 mg every 3 weeks and pediatric patients received 15 mg/kg up to a maximum 1200 mg every 3 weeks until disease progression or unacceptable toxicity. The median duration of exposure to TECENTRIQ was 8.9 months (1 to 40 months).

Serious adverse reactions occurred in 41% of patients receiving TECENTRIQ. The most frequent serious adverse reactions (>2%) were fatigue, pain in extremity, pulmonary hemorrhage, and pneumonia (4.1% each).

Dosage interruptions of TECENTRIQ due to an adverse reaction occurred in 35% of patients. The most common adverse reactions (≥3%) leading to dose interruptions were pneumonitis and pain in extremity (4.1% each).

Tables 22 and 23 summarize adverse reactions and laboratory abnormalities in Study ML39345.

Table 22: Adverse Reactions Occurring in ≥15% of Patients with ASPS Receiving TECENTRIQ in ML39345
Adverse Reaction | TECENTRIQ N = 49
Adverse Reaction | All Grades (%) | Grades 3–4 (%)
General disorders and administration site conditions
Fatigue | 55 | 2
Pyrexia | 25 | 2
Influenza like illness | 18 | 0
Gastrointestinal disorders
Nausea | 43 | 0
Vomiting | 37 | 0
Constipation | 33 | 0
Diarrhea | 27 | 2
Abdominal pain [Includes abdominal pain and abdominal pain upper] | 25 | 0
Metabolism and nutrition disorders
Decreased appetite | 22 | 2
Respiratory, Thoracic and Mediastinal
Cough [Includes cough, upper-airway cough syndrome, and productive cough] | 45 | 0
Dyspnea | 33 | 0
Rhinitis allergic | 16 | 0
Musculoskeletal and connective tissue disorders
Musculoskeletal pain [Includes arthralgia, pain in extremity, myalgia, non-cardiac chest pain, neck pain, musculoskeletal chest pain, and back pain] | 67 | 8
Skin and subcutaneous tissue disorders
Rash [Includes rash maculo-papular, rash, dermatitis acneiform, eczema, skin exfoliation, and drug eruption] | 47 | 2
Nervous system disorders
Headache | 43 | 4
Dizziness [Includes vertigo and dizziness] | 29 | 4
Vascular disorders
Hypertension | 43 | 6
Hemorrhage [Includes pulmonary hemorrhage, hemoptysis, conjunctival hemorrhage, epistaxis, hematuria, rectal hemorrhage, and laryngeal hemorrhage] | 29 | 2
Psychiatric disorders
Insomnia | 27 | 0
Anxiety | 25 | 0
Cardiac Disorders
Arrhythmia [Includes atrial fibrillation, sinus bradycardia, ventricular tachycardia, and sinus tachycardia] | 22 | 2
Endocrine disorders
Hypothyroidism [Includes hypothyroidism and blood thyroid stimulating hormone increased] | 25 | 0
Investigations
Weight decreased | 18 | 0
Weight increased | 16 | 6
Graded per NCI CTCAE v4.0

Table 23: Laboratory Abnormalities Worsening from Baseline Occurring in ≥20% of Patients with ASPS Receiving TECENTRIQ in ML39345
Laboratory Abnormality [Laboratory tests which do not have NCI CTCAE grading criteria are also included for All Grade assessments, which were performed by comparing to respective lab normal ranges.] | TECENTRIQ [The denominators used to calculate the rate varied from 4-49 for all tests of interest based on the number of patients with a baseline value and at least one on-study laboratory measurement available.]
Laboratory Abnormality [Laboratory tests which do not have NCI CTCAE grading criteria are also included for All Grade assessments, which were performed by comparing to respective lab normal ranges.] | All Grades (%) | Grades 3–4 (%)
Hematology
Decreased Hemoglobin | 63 | 0
Decreased Platelets | 27 | 0
Increased Platelets | 29 | 0
Chemistry
Increased Alkaline Phosphatase | 29 | 0
Decreased Amylase | 40 | 0
Increased Amylase | 20 | 20
Decreased Bilirubin | 49 | 0
Decreased Calcium | 47 | 0
Increased Calcium | 25 | 14
Decreased Glucose | 33 | 0
Increased Glucose | 78 | 0
Decreased Glucose (fasting) | 25 | 0
Decreased Magnesium | 21 | 0
Increased Magnesium | 26 | 26
Increased AST | 39 | 2
Increased ALT | 33 | 2
Decreased Sodium | 43 | 0
Increased Lipase | 25 | 25

6.2 Postmarketing Experience

The following adverse reactions have been identified during post-approval use of TECENTRIQ. Because these reactions are reported voluntarily from a population of uncertain size, it is not always possible to reliably estimate their frequency or establish a causal relationship to drug exposure.

- Cardiac: pericarditis, pericardial effusion, cardiac tamponade
- Musculoskeletal and Connective Tissue: tenosynovitis

8 USE IN SPECIFIC POPULATIONS

8.1 Pregnancy

Risk Summary

Based on its mechanism of action [see Clinical Pharmacology (12.1)], TECENTRIQ can cause fetal harm when administered to a pregnant woman. There are no available data on the use of TECENTRIQ in pregnant women.

Animal studies have demonstrated that inhibition of the PD-L1/PD-1 pathway can lead to increased risk of immune-related rejection of the developing fetus resulting in fetal death (see Data). Advise females of reproductive potential of the potential risk to a fetus.

In the U.S. general population, the estimated background risk of major birth defects and miscarriage in clinically recognized pregnancies is 2% to 4% and 15% to 20%, respectively.

Data

Animal Data

Animal reproduction studies have not been conducted with TECENTRIQ to evaluate its effect on reproduction and fetal development. A literature-based assessment of the effects on reproduction demonstrated that a central function of the PD-L1/PD-1 pathway is to preserve pregnancy by maintaining maternal immune tolerance to a fetus. Blockage of PD-L1 signaling has been shown in murine models of pregnancy to disrupt tolerance to a fetus and to result in an increase in fetal loss; therefore, potential risks of administering TECENTRIQ during pregnancy include increased rates of abortion or stillbirth. As reported in the literature, there were no malformations related to the blockade of PD-L1/PD-1 signaling in the offspring of these animals; however, immune-mediated disorders occurred in PD-1 and PD-L1 knockout mice. Based on its mechanism of action, fetal exposure to atezolizumab may increase the risk of developing immune-mediated disorders or altering the normal immune response.

8.2 Lactation

Risk Summary

There is no information regarding the presence of atezolizumab in human milk, the effects on the breastfed infant, or the effects on milk production. As human IgG is excreted in human milk, the potential for absorption and harm to the infant is unknown. Because of the potential for serious adverse reactions in breastfed infants from TECENTRIQ, advise women not to breastfeed during treatment and for at least 5 months after the last dose.

8.3 Females and Males of Reproductive Potential

Pregnancy Testing

Verify pregnancy status in females of reproductive potential prior to initiating TECENTRIQ [see Use in Specific Populations (8.1)].

Contraception

Females

Based on its mechanism of action, TECENTRIQ can cause fetal harm when administered to a pregnant woman [see Use in Specific Populations (8.1)]. Advise females of reproductive potential to use effective contraception during treatment with TECENTRIQ and for at least 5 months following the last dose.

Infertility

Females

Based on animal studies, TECENTRIQ may impair fertility in females of reproductive potential while receiving treatment [see Nonclinical Toxicology (13.1)].

8.4 Pediatric Use

Alveolar Soft Part Sarcoma

The safety and effectiveness of TECENTRIQ for unresectable or metastatic ASPS have been established in pediatric patients aged 2 years and older. Use of TECENTRIQ for this indication is supported by evidence from an adequate and well controlled study of TECENTRIQ in adults and 2 adolescent pediatric patients (≥12 years of age) with ASPS with additional pharmacokinetic and safety data in pediatric patients 2 years to <17 years. These data suggest that atezolizumab exposure in pediatric patients aged 2 years and older is comparable with that of adults and is expected to result in similar safety and efficacy to that of adults [see Adverse Reactions (6.1), Pharmacokinetics (12.3), Clinical Studies (14.5)]. The course of unresectable or metastatic ASPS is sufficiently similar between pediatric patients 2 to 11 years old and that of adults and adolescent patients to allow extrapolation of efficacy and safety to pediatric patients 2 years and older.

The safety and effectiveness of TECENTRIQ for ASPS have not been established in pediatric patients younger than 2 years of age.

Solid Tumors and Lymphomas

The safety and effectiveness of TECENTRIQ in pediatric patients have not been established in non-small cell lung cancer, small-cell lung cancer, hepatocellular carcinoma, or melanoma.

The safety and effectiveness of TECENTRIQ were assessed, but not established in a single-arm, multi-center, multi-cohort trial (NCT02541604) in 60 pediatric patients aged 7 months to <17 years with relapsed or progressive solid tumors and lymphomas. No new safety signals were observed in pediatric patients in this study.

8.5 Geriatric Use

TECENTRIQ as a Single-Agent

Of 2616 patients with metastatic NSCLC and other tumor types treated with single agent TECENTRIQ in clinical studies, 49% were 65 years and over and 15% were 75 years and over.

No overall differences in safety or effectiveness were observed between patients aged 65 years or older and younger patients.

TECENTRIQ in Combination with Other Antineoplastic Drugs

Of 2421 patients with NSCLC and SCLC treated with TECENTRIQ in combination with other antineoplastic drugs in clinical studies, 48% were 65 years and over and 10% were 75 years and over.

No overall differences in safety or effectiveness were observed between patients aged 65 years or older and younger patients.

TECENTRIQ in Combination with Lurbinectedin

Of the 242 patients with ES-SCLC treated with TECENTRIQ in combination with lurbinectedin in IMforte, 124 (51%) patients were 65 years of age and older, while 29 (12%) patients were 75 years of age and older. No overall differences in effectiveness were observed between older and younger patients. There was a higher incidence of Grade 3 or 4 adverse reactions (45% vs 31%) and treatment discontinuation (11% vs 0.8%) in patients ≥ 65 years of age compared to younger patients, respectively.

11 DESCRIPTION

Atezolizumab is a programmed cell death ligand 1 (PD-L1) blocking antibody. Atezolizumab is an Fc-engineered, humanized, non-glycosylated IgG1 kappa immunoglobulin that has a calculated molecular mass of 145 kDa.

TECENTRIQ (atezolizumab) injection for intravenous use is a sterile, preservative-free, colorless to slightly yellow solution in single-dose vials. Each 20 mL vial contains 1200 mg of atezolizumab and is formulated in glacial acetic acid (16.5 mg), L-histidine (62 mg), polysorbate 20 (8 mg), and sucrose (821.6 mg), with a pH of 5.8. Each 14 mL vial contains 840 mg of atezolizumab and is formulated in glacial acetic acid (11.5 mg), L-histidine (43.4 mg), polysorbate 20 (5.6 mg), and sucrose (575.1 mg) with a pH of 5.8.

12 CLINICAL PHARMACOLOGY

12.1 Mechanism of Action

PD L1 may be expressed on tumor cells and/or tumor infiltrating immune cells and can contribute to the inhibition of the anti-tumor immune response in the tumor microenvironment. Binding of PD L1 to the PD 1 and B7.1 receptors found on T cells and antigen presenting cells suppresses cytotoxic T-cell activity, T-cell proliferation and cytokine production.

Atezolizumab is a monoclonal antibody that binds to PD L1 and blocks its interactions with both PD 1 and B7.1 receptors. This releases the PD L1/PD 1 mediated inhibition of the immune response, including activation of the anti-tumor immune response without inducing antibody-dependent cellular cytotoxicity. In syngeneic mouse tumor models, blocking PD L1 activity resulted in decreased tumor growth.

In mouse models of cancer, dual inhibition of the PD-1/PD-L1 and MAPK pathways suppresses tumor growth and improves tumor immunogenicity through increased antigen presentation and T cell infiltration and activation compared to targeted therapy alone.

12.2 Pharmacodynamics

The exposure-response relationship and time course of pharmacodynamic response for the safety and effectiveness of atezolizumab have not been fully characterized.

12.3 Pharmacokinetics

Atezolizumab exposure increased dose proportionally over the dose range of 1 mg/kg to 20 mg/kg (0.07 to 1.33 times of the approved recommended doses), including a dose of 1200 mg administered every 3 weeks. Steady state was achieved after 6 to 9 weeks following multiple doses. The systemic accumulation ratio for every 2 weeks administration and every 3 weeks administration is 3.3- and 1.9- fold, respectively.

Distribution

The volume of distribution at steady state is 6.9 L.

Elimination

The clearance (CV%) is 0.2 L/day (29%) and the terminal half-life is 27 days. Atezolizumab clearance was found to decrease over time, with a mean maximal reduction (CV%) from baseline value of 17% (41%); however, the decrease in clearance was not considered clinically relevant.

Specific Populations

The following factors had no clinically significant effect on the systemic exposure of atezolizumab: age (2 to 89 years), body weight, sex, albumin levels, tumor burden, region or race, mild or moderate renal impairment [estimated glomerular filtration rate (eGFR) 30 to 89 mL/min/1.73 m^2], mild hepatic impairment (bilirubin ≤ ULN and AST > ULN or bilirubin > 1 to 1.5 × ULN and any AST), moderate hepatic impairment (bilirubin >1.5 to 3 × ULN and any AST), level of PD-L1 expression, or performance status.

Pediatric Patients

Atezolizumab serum concentrations with weight-based dosing at 15 mg/kg up to a maximum of 1200 mg every 3 weeks, in pediatric patients (2 years to <17 years) with relapsed or progressive solid tumors and lymphomas, are comparable to those of adult patients receiving 1200 mg every 3 weeks; while the exposure tended to be lower in pediatric patients less than 12 years old, this is not considered to be clinically relevant.

12.6 Immunogenicity

The observed incidence of anti-drug antibodies (ADA) is highly dependent on the sensitivity and specificity of the assay. Differences in assay methods preclude meaningful comparisons of the incidence of ADA in the studies described below with the incidence of ADA in other products.

During the first year of treatment with TECENTRIQ across 8 clinical studies, 13% to 36% of patients developed anti-atezolizumab antibodies. Median atezolizumab clearance in patients who tested positive for ADA was 19% (minimum 18%, maximum 49%) higher as compared to atezolizumab clearance in patients who tested negative for ADA; this change in clearance is not expected to be clinically significant.

In OAK and IMbrave150, exploratory analyses showed that the subset of patients who were ADA-positive appeared to have less efficacy (effect on overall survival) as compared to patients who tested negative for ADA [see Clinical Studies (14.1, 14.3)]. In study IMpower150 and IMforte, the impact of ADA on efficacy did not appear to be clinically significant [see Clinical Studies (14.1)]. In the remaining studies, there is insufficient information to characterize the effect of ADA on efficacy.

The presence of ADA did not have a clinically significant effect on the incidence or severity of adverse reactions.

Across clinical studies, the incidence of neutralizing antibodies (NAb) in ADA-positive patients was 24% to 83%. The effect of NAb on atezolizumab exposure and safety did not appear to be clinically significant. The effect of NAb on key efficacy endpoints is uncertain due to small sample sizes.

13 NONCLINICAL TOXICOLOGY

13.1 Carcinogenesis, Mutagenesis, Impairment of Fertility

No studies have been performed to test the potential of atezolizumab for carcinogenicity or genotoxicity.

Animal fertility studies have not been conducted with atezolizumab; however, an assessment of the male and female reproductive organs was included in a 26-week, repeat-dose toxicity study in cynomolgus monkeys. Weekly administration of atezolizumab to female monkeys at the highest dose tested caused an irregular menstrual cycle pattern and a lack of newly formed corpora lutea in the ovaries. This effect occurred at an estimated AUC approximately 6 times the AUC in patients receiving the recommended dose and was reversible. There was no effect on the male monkey reproductive organs.

13.2 Animal Toxicology and/or Pharmacology

In animal models, inhibition of PD-L1/PD-1 signaling increased the severity of some infections and enhanced inflammatory responses. M. tuberculosis-infected PD-1 knockout mice exhibit markedly decreased survival compared with wild-type controls, which correlated with increased bacterial proliferation and inflammatory responses in these animals. PD-L1 and PD-1 knockout mice and mice receiving PD-L1 blocking antibody have also shown decreased survival following infection with lymphocytic choriomeningitis virus.

14 CLINICAL STUDIES

14.1 Non-Small Cell Lung Cancer

Adjuvant Treatment of Stage II-IIIA NSCLC with PD-L1 Expression ≥ 1%

The efficacy of TECENTRIQ was evaluated in IMpower010 (NCT02486718), a multi-center, randomized, open-label trial for the adjuvant treatment of patients with NSCLC who had complete tumor resection and were eligible to receive cisplatin-based adjuvant chemotherapy. Eligible patients were required to have Stage IB (tumors ≥ 4 cm) – Stage IIIA NSCLC per the Union for International Cancer Control/American Joint Committee on Cancer staging system, 7th edition. Patients were excluded if they had a history of autoimmune disease; a history of idiopathic pulmonary fibrosis, organizing pneumonia, drug-induced pneumonitis, idiopathic pneumonitis, or evidence of active pneumonitis; administration of a live, attenuated vaccine within 28 days prior to randomization; administration of systemic immunostimulatory agents within 4 weeks or systemic immunosuppressive medications within 2 weeks prior to randomization.

A total of 1005 patients who had complete tumor resection and received cisplatin-based adjuvant chemotherapy were randomized (1:1) to receive TECENTRIQ 1200 mg intravenous infusion every 3 weeks for 16 cycles, unless disease recurrence or unacceptable toxicity occurred, or best supportive care (BSC). Randomization was stratified by sex, stage of disease, histology, and PD-L1 expression.

Tumor assessments were conducted at baseline of the randomization phase and every 4 months for the first year following Cycle 1, Day 1 and then every 6 months until year five, then annually thereafter.

The median age was 62 years (range: 26 to 84), and 67% of patients were male. The majority of patients were White (73%) and Asian (24%). Most patients were current or previous smokers (78%) and baseline Eastern Cooperative Oncology Group (ECOG) performance status in patients was 0 (55%) or 1 (44%). Overall, 12% of patients had Stage IB, 47% had Stage II and 41% had Stage IIIA disease. PD-L1 expression, defined as the percentage of tumor cells expressing PD-L1 as measured by the VENTANA PD-L1 (SP263) assay, was ≥ 1% in 53% of patients, <1% in 44% and unknown in 2.6%.

The primary efficacy outcome measure was disease-free survival (DFS) as assessed by the investigator. The primary efficacy analysis population (n = 476) was patients with Stage II – IIIA NSCLC with PD-L1 expression on ≥ 1% of tumor cells (PD-L1 ≥ 1% TC). DFS was defined as the time from the date of randomization to the date of occurrence of any of the following: first documented recurrence of disease, new primary NSCLC, or death due to any cause, whichever occurred first. A key secondary efficacy outcome measure was overall survival (OS) in the intent-to-treat population.

At the time of the interim DFS analysis, the study demonstrated a statistically significant improvement in DFS in the PD-L1 ≥ 1% TC, Stage II – IIIA patient population.

Efficacy results are presented in Table 24 and Figure 1.

Table 24: Efficacy Results from IMpower010 in Patients with Stage II - IIIA NSCLC with PD-L1 expression ≥ 1% TC
 | Arm A: TECENTRIQ N = 248 | Arm B: Best Supportive Care N = 228
Disease-Free Survival
Number of events (%) | 88 (35) | 105 (46)
Median, months | NR | 35.3
(95% CI) | (36.1, NE) | (29.0, NE)
Hazard ratio [Stratified by stage, sex, and histology] (95% CI) | 0.66 (0.50, 0.88)
p-value | 0.004
CI = Confidence interval, NE = Not estimable, NR = Not reached

In a pre-specified secondary subgroup analysis of patients with PD-L1 TC ≥ 50% Stage II – IIIA NSCLC (n=229), the median DFS was not reached (95% CI: 42.3 months, NE) for patients in the TECENTRIQ arm and was 35.7 months (95% CI: 29.7, NE) for patients in the best supportive care arm, with a HR of 0.43 (95% CI: 0.27, 0.68). In an exploratory subgroup analysis of patients with PD-L1 TC 1-49% Stage II – IIIA NSCLC (n=247), the median DFS was 32.8 months (95% CI: 29.4, NE) for patients in the TECENTRIQ arm and 31.4 months (95% CI: 24.0, NE) for patients in the best supportive care arm, with a HR of 0.87 (95% CI: 0.60, 1.26).

Figure 1: Kaplan-Meier Plot of Disease-Free Survival in IMpower010 in Patients with Stage II – IIIA NSCLC with PD-L1 expression ≥ 1% TC

At the time of the DFS interim analysis, 19% of patients in the PD-L1 ≥1% TC Stage II – IIIA patient population had died. An exploratory analysis of OS in this population resulted in a stratified HR of 0.77 (95% CI: 0.51, 1.17).

Metastatic Chemotherapy-Naïve NSCLC with High PD-L1 Expression

The efficacy of TECENTRIQ was evaluated in IMpower110 (NCT02409342), a multicenter, international, randomized, open-label trial in patients with stage IV NSCLC whose tumors express PD-L1 (PD-L1 stained ≥ 1% of tumor cells [TC ≥ 1%] or PD-L1 stained tumor-infiltrating immune cells [IC] covering ≥ 1% of the tumor area [IC ≥ 1%]), who had received no prior chemotherapy for metastatic disease. PD-L1 tumor status was determined based on immunohistochemistry (IHC) testing using the VENTANA PD-L1 (SP142) Assay. The evaluation of efficacy is based on the subgroup of patients with high PD-L1 expression (TC ≥ 50% or IC ≥ 10%), excluding those with EGFR or ALK genomic tumor aberrations. The trial excluded patients with a history of autoimmune disease, administration of a live attenuated vaccine within 28 days prior to randomization, active or untreated CNS metastases, administration of systemic immunostimulatory agents within 4 weeks or systemic immunosuppressive medications within 2 weeks prior to randomization.

Randomization was stratified by sex, ECOG performance status, histology (non-squamous vs. squamous) and PD-L1 expression (TC ≥ 1% and any IC vs. TC < 1% and IC ≥ 1%). Patients were randomized (1:1) to receive one of the following treatment arms:

- Arm A: TECENTRIQ 1200 mg every 3 weeks until disease progression or unacceptable toxicity
- Arm B: Platinum-based chemotherapy

Arm B platinum-based chemotherapy regimens for non-squamous NSCLC consisted of cisplatin (75 mg/m^2) and pemetrexed (500 mg/m^2) OR carboplatin (AUC 6 mg/mL/min) and pemetrexed (500 mg/m^2) on Day 1 of each 21-day cycle for a maximum of 4 or 6 cycles followed by pemetrexed (500 mg/m^2) until disease progression or unacceptable toxicity.

Arm B platinum-based chemotherapy regimens for squamous NSCLC consisted of cisplatin (75 mg/m^2) on Day 1 with gemcitabine (1250 mg/m^2) on Days 1 and 8 of each 21-day cycle OR carboplatin (AUC 5 mg/mL/min) on Day 1 with gemcitabine (1000 mg/m^2) on Days 1 and 8 of each 21-day cycle for a maximum of 4 or 6 cycles followed by best supportive care until disease progression or unacceptable toxicity.

Administration of TECENTRIQ was permitted beyond RECIST-defined disease progression. Tumor assessments were conducted every 6 weeks for the first 48 weeks following Cycle 1, Day 1 and then every 9 weeks thereafter. Tumor specimens were evaluated prospectively using the VENTANA PD-L1 (SP142) Assay at a central laboratory and the results were used to define subgroups for pre-specified analyses.

The major efficacy outcome measure was overall survival (OS) sequentially tested in the following subgroups of patients, excluding those with EGFR or ALK genomic tumor aberrations: TC ≥50% or IC ≥10%; TC ≥5% or IC ≥5%; and TC ≥1% or IC ≥1%.

Among the 205 chemotherapy-naïve patients with stage IV NSCLC with high PD-L1 expression (TC ≥ 50% or IC ≥ 10%) excluding those with EGFR or ALK genomic tumor aberrations, the median age was 65.0 years (range: 33 to 87), and 70% of patients were male. The majority of patients were White (82%) and Asian (17%). Baseline ECOG performance status was 0 (36%) or 1 (64%); 88% were current or previous smokers; and 76% of patients had non-squamous disease while 24% of patients had squamous disease.

The trial demonstrated a statistically significant improvement in OS for patients with high PD-L1 expression (TC ≥50% or IC ≥10%) at the time of the OS interim analysis. There was no statistically significant difference in OS for the other two PD-L1 subgroups (TC ≥5% or IC ≥5%; and TC ≥1% or IC ≥1%) at the interim or final analyses. Efficacy results for patients with NSCLC with high PD-L1 expression are presented in Table 25 and Figure 2.

Table 25: Efficacy Results from IMpower110 in Patients with NSCLC with High PD-L1 Expression (TC ≥ 50% or IC ≥ 10%) and without EGFR or ALK Genomic Tumor Aberrations
 | Arm A: TECENTRIQ N = 107 | Arm B: Platinum-Based Chemotherapy N = 98
 | Overall Survival [Based on OS interim analysis. The median survival follow-up time in patients was 15.7 months.]
Deaths (%) | 44 (41%) | 57 (58%)
Median, months | 20.2 | 13.1
(95% CI) | (16.5, NE) | (7.4, 16.5)
Hazard ratio [Stratified by sex and ECOG performance status] (95% CI) | 0.59 (0.40, 0.89)
p-value [Based on the stratified log-rank test compared to Arm A] | 0.0106 [Compared to the allocated alpha of 0.0413 (two-sided) for this interim analysis.]
CI=confidence interval; NE=not estimable

Figure 2: Kaplan-Meier Plot of Overall Survival in IMpower110 in Patients with NSCLC with High PD-L1 Expression (TC ≥ 50% or IC ≥ 10%) and without EGFR or ALK Genomic Tumor Aberrations

Investigator-assessed PFS showed an HR of 0.63 (95% CI: 0.45, 0.88), with median PFS of 8.1 months (95% CI: 6.8, 11.0) in the TECENTRIQ arm and 5 months (95% CI: 4.2, 5.7) in the platinum-based chemotherapy arm. The investigator-assessed confirmed ORR was 38% (95% CI: 29%, 48%) in the TECENTRIQ arm and 29% (95% CI: 20%, 39%) in the platinum-based chemotherapy arm.

Metastatic Chemotherapy-Naive Non-Squamous NSCLC

IMpower150

The efficacy of TECENTRIQ with bevacizumab, paclitaxel, and carboplatin was evaluated in IMpower150 (NCT02366143), a multicenter, international, randomized (1:1:1), open-label trial in patients with metastatic non-squamous NSCLC. Patients with stage IV non-squamous NSCLC who had received no prior chemotherapy for metastatic disease but could have received prior EGFR or ALK kinase inhibitor if appropriate, regardless of PD-L1 or T-effector gene (tGE) status and ECOG performance status 0 or 1 were eligible. The trial excluded patients with a history of autoimmune disease, administration of a live attenuated vaccine within 28 days prior to randomization, active or untreated CNS metastases, administration of systemic immunostimulatory agents within 4 weeks or systemic immunosuppressive medications within 2 weeks prior to randomization, or clear tumor infiltration into the thoracic great vessels or clear cavitation of pulmonary lesions as seen on imaging. Randomization was stratified by sex, presence of liver metastases, and PD-L1 expression status on tumor cells (TC) and tumor-infiltrating immune cells (IC) as follows: TC3 and any IC vs. TC0/1/2 and IC2/3 vs. TC0/1/2 and IC0/1. Patients were randomized to one of the following three treatment arms:

- Arm A: TECENTRIQ 1200 mg, paclitaxel 175 mg/m^2 or 200 mg/m^2 and carboplatin AUC 6 mg/mL/min on Day 1 of each 21-day cycle for a maximum of 4 or 6 cycles
- Arm B: TECENTRIQ 1200 mg, bevacizumab 15 mg/kg, paclitaxel 175 mg/m^2 or 200 mg/m^2, and carboplatin AUC 6 mg/mL/min on Day 1 of each 21-day cycle for a maximum of 4 or 6 cycles
- Arm C: bevacizumab 15 mg/kg, paclitaxel 175 mg/m^2 or 200 mg/m^2, and carboplatin AUC 6 mg/mL/min on Day 1 of each 21-day cycle for a maximum of 4 or 6 cycles

Patients who had not experienced disease progression following the completion or cessation of platinum-based chemotherapy, received:

- Arm A: TECENTRIQ 1200 mg intravenously on Day 1 of each 21-day cycle until disease progression or unacceptable toxicity
- Arm B: TECENTRIQ 1200 mg and bevacizumab 15 mg/kg intravenously on Day 1 of each 21-day cycle until disease progression or unacceptable toxicity
- Arm C: bevacizumab 15 mg/kg intravenously on Day 1 of each 21-day cycle until disease progression or unacceptable toxicity

Tumor assessments were conducted every 6 weeks for the first 48 weeks following Cycle 1, Day 1 and then every 9 weeks thereafter. Tumor specimens were evaluated prior to randomization for PD-L1 tumor expression using the VENTANA PD-L1 (SP142) assay at a central laboratory. Tumor tissue was collected at baseline for expression of tGE signature and evaluation was performed using a clinical trial assay in a central laboratory prior to the analysis of efficacy outcome measures.

Major efficacy outcome measures for comparison of Arms B and C were progression free survival (PFS) by RECIST v1.1 in the tGE-WT (patients with high expression of T-effector gene signature [tGE], excluding those with EGFR- and ALK-positive NSCLC [WT]) and in the ITT-WT subpopulations and overall survival (OS) in the ITT-WT subpopulation. Additional efficacy outcome measures for comparison of Arms B and C or Arms A and C were PFS and OS in the ITT population, OS in the tGE-WT subpopulation, and ORR/DoR in the tGE-WT and ITT-WT subpopulations.

A total of 1202 patients were enrolled across the three arms of whom 1045 were in the ITT-WT subpopulation and 447 were in the tGE-WT subpopulation. The demographic information is limited to the 800 patients enrolled in Arms B and C where efficacy has been demonstrated. The median age was 63 years (range: 31 to 90), and 60% of patients were male. The majority of patients were White (82%), 13% of patients were Asian, 10% were Hispanic, and 2% of patients were Black. Clinical sites in Asia (enrolling 13% of the study population) received paclitaxel at a dose of 175 mg/m^2 while the remaining 87% received paclitaxel at a dose of 200 mg/m^2. Approximately 14% of patients had liver metastases at baseline, and most patients were current or previous smokers (80%). Baseline ECOG performance status was 0 (43%) or 1 (57%). PD-L1 was TC3 and any IC in 12%, TC0/1/2 and IC2/3 in 13%, and TC0/1/2 and IC0/1 in 75%. The demographics for the 696 patients in the ITT-WT subpopulation were similar to the ITT population except for the absence of patients with EGFR- or ALK- positive NSCLC.

The trial demonstrated a statistically significant improvement in PFS between Arms B and C in both the tGE-WT and ITT-WT subpopulations, but did not demonstrate a significant difference for either subpopulation between Arms A and C based on the final PFS analyses. In the interim analysis of OS, a statistically significant improvement was observed for Arm B compared to Arm C, but not for Arm A compared to Arm C. Efficacy results for the ITT-WT subpopulation are presented in Table 26 and Figure 3.

Table 26: Efficacy Results in ITT-WT Population in IMpower150
 | Arm C: Bevacizumab, Paclitaxel and Carboplatin | Arm B: TECENTRIQ with Bevacizumab, Paclitaxel, and Carboplatin | Arm A: TECENTRIQ with Paclitaxel, and Carboplatin
 | N = 337 | N = 359 | N = 349
Overall Survival [Based on OS interim analysis]
Deaths (%) | 197 (59%) | 179 (50%) | 179 (51%)
Median, months | 14.7 | 19.2 | 19.4
(95% CI) | (13.3, 16.9) | (17.0, 23.8) | (15.7, 21.3)
Hazard ratio [Stratified by sex, presence of liver metastases, and PD-L1 expression status on TC and IC] (95% CI) | --- | 0.78 (0.64, 0.96) | 0.84 (0.72, 1.08)
p-value [Based on the stratified log-rank test compared to Arm C] | --- | 0.016 [Compared to the allocated α=0.0174 (two sided) for this interim analysis] | 0.204 [Compared to the allocated α=0.0128 (two sided) for this interim analysis]
Progression-Free Survival [As determined by independent review facility (IRF) per RECIST v1.1 (Response Evaluation Criteria in Solid Tumors v1.1)]
Number of events (%) | 247 (73%) | 247 (69%) | 245 (70%)
Median, months | 7.0 | 8.5 | 6.7
(95% CI) | (6.3, 7.9) | (7.3, 9.7) | (5.6, 6.9)
Hazard ratio (95% CI) | --- | 0.71 (0.59, 0.85) | 0.94 (0.79, 1.13)
p-value | --- | 0.0002 [Compared to the allocated α=0.006 (two sided) for the final PFS analysis] | 0.5219
Objective Response Rate
Number of responders (%) | 142 (42%) | 196 (55%) | 150 (43%)
(95% CI) | (37, 48) | (49, 60) | (38, 48)
Complete Response | 3 (1%) | 14 (4%) | 9 (3%)
Partial Response | 139 (41%) | 182 (51%) | 141 (40%)
Duration of Response | n = 142 | n = 196 | n = 150
Median, months | 6.5 | 10.8 | 9.5
(95% CI) | (5.6, 7.6) | (8.4, 13.9) | (7.0, 13.0)
CI=confidence interval

Figure 3: Kaplan-Meier Curves for Overall Survival in ITT-WT Population in IMpower150

Exploratory analyses showed that the subset of patients in the four drug regimen arm who were ADA positive by week 4 (30%) appeared to have similar efficacy (effect on overall survival) as compared to patients who tested negative for treatment-emergent ADA by week 4 (70%) [see Clinical Pharmacology (12.6)]. In an exploratory analysis, propensity score matching was conducted to compare ADA positive patients in the TECENTRIQ, bevacizumab, paclitaxel, and carboplatin arm with a matched population in the bevacizumab, paclitaxel, and carboplatin arm. Similarly ADA negative patients in the TECENTRIQ, bevacizumab, paclitaxel, and carboplatin arm were compared with a matched population in the bevacizumab, paclitaxel, and carboplatin arm. Propensity score matching factors were: baseline sum of longest tumor size (BSLD), baseline ECOG, baseline albumin, baseline LDH, sex, tobacco history, metastatic site, TC level, and IC level. The hazard ratio comparing the ADA-positive subgroup with its matched control was 0.69 (95% CI: 0.44, 1.07). The hazard ratio comparing the ADA-negative subgroup with its matched control was 0.64 (95% CI: 0.46, 0.90).

IMpower130

The efficacy of TECENTRIQ with paclitaxel protein-bound and carboplatin was evaluated in IMpower130 (NCT02367781), a multicenter, randomized (2:1), open-label trial in patients with stage IV non-squamous NSCLC. Patients with Stage IV non-squamous NSCLC who had received no prior chemotherapy for metastatic disease, but could have received prior EGFR or ALK kinase inhibitor, if appropriate, were eligible. The trial excluded patients with history of autoimmune disease, administration of live attenuated vaccine within 28 days prior to randomization, administration of immunostimulatory agents within 4 weeks or systemic immunosuppressive medications within 2 weeks prior to randomization, and active or untreated CNS metastases. Randomization was stratified by sex, presence of liver metastases, and PD-L1 tumor expression according to the VENTANA PD-L1 (SP142) assay as follows: TC3 and any IC vs. TC0/1/2 and IC2/3 vs. TC0/1/2 and IC0/1. Patients were randomized to one of the following treatment regimens:

- TECENTRIQ 1200 mg on Day 1, paclitaxel protein-bound 100 mg/m^2 on Days 1, 8, and 15, and carboplatin AUC 6 mg/mL/min on Day 1 of each 21-day cycle for a maximum of 4 or 6 cycles followed by TECENTRIQ 1200 mg once every 3 weeks until disease progression or unacceptable toxicity, or
- Paclitaxel protein-bound 100 mg/m^2 on Days 1, 8 and 15 and carboplatin AUC 6 mg/mL/min on Day 1 of each 21-day cycle for a maximum of 4 or 6 cycles followed by best supportive care or pemetrexed.

Tumor assessments were conducted every 6 weeks for the first 48 weeks, then every 9 weeks thereafter. Major efficacy outcome measures were PFS by RECIST v1.1 and OS in the subpopulation of patients evaluated for and documented to have no EGFR or ALK genomic tumor aberrations (ITT-WT).

A total of 724 patients were enrolled; of these, 681 (94%) were in the ITT-WT population. The median age was 64 years (range: 18 to 86) and 59% were male. The majority of patients were white (90%), 2% of patients were Asian, 5% were Hispanic, and 4% were Black. Baseline ECOG performance status was 0 (41%) or 1 (58%). Most patients were current or previous smokers (90%). PD-L1 tumor expression was TC0/1/2 and IC0/1 in 73%; TC3 and any IC in 14%; and TC0/1/2 and IC2/3 in 13%.

Efficacy results for the ITT-WT population are presented in Table 27 and Figure 4.

Table 27: Efficacy Results from IMpower130
 | TECENTRIQ with Paclitaxel Protein-Bound and Carboplatin | Paclitaxel Protein-Bound and Carboplatin
Overall Survival [Based on OS interim analysis] | n=453 | n=228
Deaths (%) | 228 (50%) | 131 (57%)
Median, months | 18.6 | 13.9
(95% CI) | (15.7, 21.1) | (12.0, 18.7)
Hazard ratio [Stratified by sex and PD-L1 tumor expression on tumor cells (TC) and tumor infiltrating cells (IC)] (95% CI) | 0.80 (0.64, 0.99)
p-value [Based on the stratified log-rank test] | 0.0384 [Compared to the allocated α=0.0428 (two sided) for this interim analysis]
Progression-Free Survival [As determined by independent review facility (IRF) per RECIST v1.1 (Response Evaluation Criteria in Solid Tumors v1.1)] | n=453 | n=228
Number of events (%) | 330 (73%) | 177 (78%)
Median, months | 7.2 | 6.5
(95% CI) | (6.7, 8.3) | (5.6, 7.4)
Hazard ratio (95% CI) | 0.75 (0.63, 0.91)
p-value | 0.0024 [Compared to the allocated α=0.006 (two sided) for the final PFS analysis]
Overall Response Rate, [Confirmed response] | n=453 | n=228
Number of responders (%) | 207 (46%) | 74 (32%)
(95% CI) | (41, 50) | (26, 39)
Complete Response | 22 (5%) | 2 (1%)
Partial Response | 185 (41%) | 72 (32%)
Duration of Response, | n=207 | n=74
Median, months | 10.8 | 7.8
(95% CI) | (9.0, 14.4) | (6.8, 10.9)
CI=confidence interval

Figure 4: Kaplan-Meier Curves for Overall Survival in IMpower130

Previously Treated Metastatic NSCLC

OAK

The efficacy of TECENTRIQ was evaluated in a multicenter, international, randomized (1:1), open-label study (OAK; NCT02008227) conducted in patients with locally advanced or metastatic NSCLC whose disease progressed during or following a platinum-containing regimen. Patients with a history of autoimmune disease, symptomatic or corticosteroid-dependent brain metastases, or requiring systemic immunosuppression within 2 weeks prior to enrollment were ineligible. Randomization was stratified by PD-L1 expression tumor-infiltrating immune cells (IC), the number of prior chemotherapy regimens (1 vs. 2), and histology (squamous vs. non-squamous).

Patients were randomized to receive TECENTRIQ 1200 mg intravenously every 3 weeks until unacceptable toxicity, radiographic progression, or clinical progression or docetaxel 75 mg/m^2 intravenously every 3 weeks until unacceptable toxicity or disease progression. Tumor assessments were conducted every 6 weeks for the first 36 weeks and every 9 weeks thereafter. Major efficacy outcome measure was overall survival (OS) in the first 850 randomized patients and OS in the subgroup of patients with PD-L1-expressing tumors (defined as ≥ 1% PD-L1 expression on tumor cells [TC] or immune cells [IC]). Additional efficacy outcome measures were OS in all randomized patients (n = 1225), OS in subgroups based on PD-L1 expression, overall response rate (ORR), and progression free survival as assessed by the investigator per RECIST v.1.1.

Among the first 850 randomized patients, the median age was 64 years (33 to 85 years) and 47% were ≥ 65 years old; 61% were male; 70% were White and 21% were Asian; 15% were current smokers and 67% were former smokers; and 37% had baseline ECOG performance status (PS) of 0 and 63% had a baseline ECOG PS of 1. Nearly all (94%) had metastatic disease, 74% had non-squamous histology, 75% had received only one prior platinum-based chemotherapy regimen, and 55% of patients had PD-L1-expressing tumors.

Efficacy results are presented in Table 28 and Figure 5.

Table 28: Efficacy Results in OAK
 | TECENTRIQ | Docetaxel
Overall Survival in first 850 patients
Number of patients | N=425 | N=425
Deaths (%) | 271 (64%) | 298 (70%)
Median, months | 13.8 | 9.6
(95% CI) | (11.8, 15.7) | (8.6, 11.2)
Hazard ratio [Stratified by PD-L1 expression in tumor infiltrating immune cells, the number of prior chemotherapy regimens, and histology] (95% CI) | 0.74 (0.63, 0.87)
p-value [Based on the stratified log-rank test] | 0.0004 [Compared to the pre-specified allocated α of 0.03 for this analysis]
Progression-Free Survival
Number of Patients | N=425 | N=425
Events (%) | 380 (89%) | 375 (88%)
Progression (%) | 332 (78%) | 290 (68%)
Deaths (%) | 48 (11%) | 85 (20%)
Median, months | 2.8 | 4.0
(95% CI) | (2.6, 3.0) | (3.3, 4.2)
Hazard ratio (95% CI) | 0.95 (0.82, 1.10)
Overall Response Rate [Per RECIST v1.1 (Response Evaluation Criteria in Solid Tumors v1.1)]
Number of Patients | N=425 | N=425
ORR, n (%) | 58 (14%) | 57 (13%)
(95% CI) | (11%, 17%) | (10%, 17%)
Complete Response | 6 (1%) | 1 (0.2%)
Partial Response | 52 (12%) | 56 (13%)
Duration of Response | N=58 | N=57
Median, months | 16.3 | 6.2
(95% CI) | (10.0, NE) | (4.9, 7.6)
Overall Survival in all 1225 patients
Number of patients | N=613 | N=612
Deaths (%) | 384 (63%) | 409 (67%)
Median, months | 13.3 | 9.8
(95% CI) | (11.3, 14.9) | (8.9, 11.3)
Hazard ratio (95% CI) | 0.79 (0.69, 0.91)
p-value | 0.0013 [Compared to the allocated α of 0.0177 for this interim analysis based on 86% information using O'Brien-Fleming boundary]
CI=confidence interval; NE=not estimable

Figure 5: Kaplan-Meier Curves of Overall Survival in the First 850 Patients Randomized in OAK

Tumor specimens were evaluated prospectively using the VENTANA PD-L1 (SP142) Assay at a central laboratory and the results were used to define the PD-L1 expression subgroups for pre-specified analyses. Of the 850 patients, 16% were classified as having high PD-L1 expression, defined as having PD-L1 expression on ≥ 50% of TC or ≥ 10% of IC. In an exploratory efficacy subgroup analysis of OS based on PD-L1 expression, the hazard ratio was 0.41 (95% CI: 0.27, 0.64) in the high PD-L1 expression subgroup and 0.82 (95% CI: 0.68, 0.98) in patients who did not have high PD-L1 expression.

Exploratory analyses showed that the subset of patients who were ADA positive by week 4 (21%) appeared to have less efficacy (effect on overall survival) as compared to patients who tested negative for treatment-emergent ADA by week 4 (79%) [see Clinical Pharmacology (12.6)]. ADA positive patients by week 4 appeared to have similar OS compared to docetaxel-treated patients. In an exploratory analysis, propensity score matching was conducted to compare ADA positive patients in the TECENTRIQ arm with a matched population in the docetaxel arm and ADA negative patients in the TECENTRIQ arm with a matched population in the docetaxel arm. Propensity score matching factors were: baseline sum of longest tumor size (BSLD), baseline ECOG, histology (squamous vs. non-squamous), baseline albumin, baseline LDH, gender, tobacco history, metastases status (advanced or local), metastatic site, TC level, and IC level. The hazard ratio comparing the ADA positive subgroup with its matched control was 0.89 (95% CI: 0.61, 1.3). The hazard ratio comparing the ADA negative subgroup with its matched control was 0.68 (95% CI: 0.55, 0.83).

14.2 Small Cell Lung Cancer

IMpower133

The efficacy of TECENTRIQ with carboplatin and etoposide was investigated in IMpower133 (NCT02763579), a randomized (1:1), multicenter, double-blind, placebo-controlled trial in 403 patients with ES-SCLC. IMpower133 enrolled patients with ES-SCLC who had received no prior chemotherapy for extensive stage disease and ECOG performance status 0 or 1. The trial excluded patients with active or untreated CNS metastases, history of autoimmune disease, administration of a live, attenuated vaccine within 4 weeks prior to randomization, or administration of systemic immunosuppressive medications within 1 week prior to randomization. Randomization was stratified by sex, ECOG performance status, and presence of brain metastases. Patients were randomized to receive one of the following two treatment arms:

- TECENTRIQ 1200 mg and carboplatin AUC 5 mg/mL/min on Day 1 and etoposide 100 mg/m^2 intravenously on Days 1, 2 and 3 of each 21-day cycle for a maximum of 4 cycles followed by TECENTRIQ 1200 mg once every 3 weeks until disease progression or unacceptable toxicity, or
- placebo and carboplatin AUC 5 mg/mL/min on Day 1 and etoposide 100 mg/m^2 intravenously on Days 1, 2, and 3 of each 21-day cycle for a maximum of 4 cycles followed by placebo once every 3 weeks until disease progression or unacceptable toxicity.

Administration of TECENTRIQ was permitted beyond RECIST-defined disease progression. Tumor assessments were conducted every 6 weeks for the first 48 weeks following Cycle 1, Day 1 and then every 9 weeks thereafter. Patients treated beyond disease progression had tumor assessment conducted every 6 weeks until treatment discontinuation.

Major efficacy outcome measures were OS and PFS as assessed by investigator per RECIST v1.1 in the intent-to-treat population. Additional efficacy outcome measures included ORR and DoR as assessed by investigator per RECIST v1.1.

A total of 403 patients were randomized, including 201 to the TECENTRIQ arm and 202 to the chemotherapy alone arm. The median age was 64 years (range 26 to 90) and 65% were male. The majority of patients were White (80%); 17% were Asian, 4% were Hispanic and 1% were Black. Baseline ECOG performance status was 0 (35%) or 1 (65%); 9% of patients had a history of brain metastases, and 97% were current or previous smokers.

Efficacy results are presented in Table 29 and Figure 6.

Table 29: Efficacy Results from IMpower133
 | TECENTRIQ with Carboplatin and Etoposide | Placebo with Carboplatin and Etoposide
Overall Survival | N=201 | N=202
Deaths (%) | 104 (52%) | 134 (66%)
Median, months | 12.3 | 10.3
(95% CI) | (10.8, 15.9) | (9.3, 11.3)
Hazard ratio [Stratified by sex and ECOG performance status] (95% CI) | 0.70 (0.54, 0.91)
p-value [Based on the stratified log-rank test] , [Compared to the allocated α of 0.0193 for this interim analysis based on 78% information using O'Brien-Fleming boundary] | 0.0069
Progression-Free Survival [As determined by investigator assessment] , [per RECIST v1.1 (Response Evaluation Criteria in Solid Tumors v1.1)] | N=201 | N=202
Number of events (%) | 171 (85%) | 189 (94%)
Median, months | 5.2 | 4.3
(95% CI) | (4.4, 5.6) | (4.2, 4.5)
Hazard ratio (95% CI) | 0.77 (0.62, 0.96)
p-value, [Compared to the allocated α of 0.05 for this analysis] | 0.0170
Objective Response Rate,, [Confirmed response] | N=201 | N=202
Number of responders (%) | 121 (60%) | 130 (64%)
(95% CI) | (53, 67) | (57, 71)
Complete Response (%) | 5 (2%) | 2 (1%)
Partial Response (%) | 116 (58%) | 128 (63%)
Duration of Response,, | N=121 | N=130
Median, months | 4.2 | 3.9
(95% CI) | (4.1, 4.5) | (3.1, 4.2)
CI=confidence interval

Figure 6: Kaplan-Meier Plot of Overall Survival in IMpower133

IMforte

The efficacy of TECENTRIQ in combination with lurbinectedin as maintenance treatment was evaluated in IMforte (NCT05091567), a randomized, multicenter, open-label study in patients with ES-SCLC. Patients were eligible if their disease had not progressed after completion of four cycles of TECENTRIQ, carboplatin and etoposide (induction treatment) and they had an ECOG performance status of 0 or 1. The trial excluded patients with CNS metastases, history of autoimmune disease, or administration of systemic immunosuppressive medications within 1 week prior to enrollment. Unless contraindicated, primary prophylaxis with granulocyte colony-stimulating factor (G-CSF) was mandated for patients assigned to the TECENTRIQ with lurbinectedin arm.

The trial randomized 483 patients who had not experienced disease progression following the completion of four cycles of TECENTRIQ with carboplatin and etoposide to one of the following two treatment arms:

- TECENTRIQ 1200 mg IV in combination with lurbinectedin 3.2 mg/m^2 IV once every 3 weeks until disease progression or unacceptable toxicity, or
- TECENTRIQ 1200 mg IV once every 3 weeks until disease progression or unacceptable toxicity

Randomization was stratified by ECOG performance status prior to randomization (0 vs. 1), lactate dehydrogenase (LDH) (≤ ULN vs. > ULN) prior to randomization, presence of liver metastases prior to initial study enrollment (yes vs. no), and prior receipt of prophylactic cranial irradiation (yes vs. no).

The major efficacy outcome measures were OS and PFS by Independent Review Facility (IRF) per RECIST v1.1.

A total of 483 patients were randomized, including 242 to the TECENTRIQ with lurbinectedin arm and 241 to the TECENTRIQ arm. The median age was 66 years (range 35 to 85 years); 63% male; 82% White; 13% Asian; 0.8% were Black or African American; 7% were of Hispanic or Latino ethnicity and 98% were current or previous smokers. Baseline ECOG performance status was 0 (43%) or 1 (57%).

Efficacy results are presented in Table 30 and Figures 7 and 8.

Table 30: Efficacy Results from IMforte
 | TECENTRIQ with Lurbinectedin N=242 | TECENTRIQ N=241
Overall Survival [Measured from the time of randomization]
Deaths (%) | 113 (47%) | 136 (56%)
Median, months | 13.2 | 10.6
(95% CI) | (11.9, 16.4) | (9.5, 12.2)
Hazard ratio [Stratified by ECOG performance status, LDH level, presence of liver metastases and prior receipt of prophylactic cranial irradiation] (95% CI) | 0.73 (0.57, 0.95)
p-value [Based on the stratified log-rank test] , [Compared to the allocated alpha of 0.0313 (two-sided) for this interim OS analysis.] | 0.0174
Progression-Free Survival , [As determined by an IRF] , [per RECIST v1.1 (Response Evaluation Criteria in Solid Tumors v1.1)]
Number of events (%) | 174 (72%) | 202 (84%)
Median, months | 5.4 | 2.1
(95% CI) | (4.2, 5.8) | (1.6, 2.7)
Hazard ratio (95% CI) | 0.54 (0.43, 0.67)
p-value, [Compared to the allocated alpha of 0.001 (two- sided) for this final PFS analysis.] | <0.0001
CI=confidence interval

Figure 7: Kaplan-Meier Plot of IRF-assessed Progression-Free Survival in IMforte

Figure 8: Kaplan-Meier Plot of Overall Survival in IMforte

14.3 Hepatocellular Carcinoma

The efficacy of TECENTRIQ in combination with bevacizumab was investigated in IMbrave150 (NCT03434379), a multicenter, international, open-label, randomized trial in patients with locally advanced unresectable and/or metastatic hepatocellular carcinoma who have not received prior systemic therapy. Randomization was stratified by geographic region (Asia excluding Japan vs. rest of world), macrovascular invasion and/or extrahepatic spread (presence vs. absence), baseline AFP (<400 vs. ≥400 ng/mL), and by ECOG performance status (0 vs. 1).

A total of 501 patients were randomized (2:1) to receive either TECENTRIQ as an intravenous infusion of 1200 mg, followed by 15 mg/kg bevacizumab, on the same day every 3 weeks or sorafenib 400 mg given orally twice daily, until disease progression or unacceptable toxicity. Patients could discontinue either TECENTRIQ or bevacizumab (e.g., due to adverse events) and continue on single-agent therapy until disease progression or unacceptable toxicity associated with the single-agent.

The study enrolled patients who were ECOG performance score 0 or 1 and who had not received prior systemic treatment. Patients were required to be evaluated for the presence of varices within 6 months prior to treatment, and were excluded if they had variceal bleeding within 6 months prior to treatment, untreated or incompletely treated varices with bleeding, or high risk of bleeding. Patients with Child-Pugh B or C cirrhosis, moderate or severe ascites; history of hepatic encephalopathy; a history of autoimmune disease; administration of a live, attenuated vaccine within 4 weeks prior to randomization; administration of systemic immunostimulatory agents within 4 weeks or systemic immunosuppressive medications within 2 weeks prior to randomization; or untreated or corticosteroid-dependent brain metastases were excluded. Tumor assessments were performed every 6 weeks for the first 54 weeks and every 9 weeks thereafter.

The demographics and baseline disease characteristics of the study population were balanced between the treatment arms. The median age was 65 years (range: 26 to 88) and 83% of patients were male. The majority of patients were Asian (57%) or White (35%); 40% were from Asia (excluding Japan). Approximately 75% of patients presented with macrovascular invasion and/or extrahepatic spread and 37% had a baseline AFP ≥400 ng/mL. Baseline ECOG performance status was 0 (62%) or 1 (38%). HCC risk factors were Hepatitis B in 48% of patients, Hepatitis C in 22%, and 31% of patients had non-viral liver disease. The majority of patients had BCLC stage C (82%) disease at baseline, while 16% had stage B, and 3% had stage A.

The major efficacy outcome measures were overall survival (OS) and independent review facility (IRF)-assessed progression free survival (PFS) per RECIST v1.1. Additional efficacy outcome measures were IRF-assessed overall response rate (ORR) per RECIST and mRECIST.

Efficacy results are presented in Table 31 and Figure 9.

Table 31: Efficacy Results from IMbrave150
 | TECENTRIQ in combination with Bevacizumab (N= 336) | Sorafenib (N=165)
Overall Survival
Number of deaths (%) | 96 (29) | 65 (39)
Median OS in months (95% CI) | NE (NE, NE) | 13.2 (10.4, NE)
Hazard ratio [Stratified by geographic region (Asia excluding Japan vs. rest of world), macrovascular invasion and/or extrahepatic spread (presence vs. absence), and baseline AFP (<400 vs. ≥400 ng/mL)] (95% CI) | 0.58 (0.42, 0.79)
p-value [Based on two-sided stratified log-rank test; as compared to significance level 0.004 (2-sided) based on 161/312=52% information using the OBF method] | 0.0006
Progression-Free Survival [Per independent radiology review]
Number of events (%) | 197 (59) | 109 (66)
Median PFS in months (95% CI) | 6.8 (5.8, 8.3) | 4.3 (4.0, 5.6)
Hazard ratio (95% CI) | 0.59 (0.47, 0.76)
p-value | <0.0001
Overall Response Rate, [Confirmed responses] (ORR), RECIST 1.1
Number of responders (%) | 93 (28) | 19 (12)
(95% CI) | (23, 33) | (7,17)
p-value [Based on two-sided Cochran-Mantel-Haesnszel test] | <0.0001
Complete responses, n (%) | 22 (7) | 0
Partial responses, n (%) | 71 (21) | 19 (12)
Duration of Response, (DOR) RECIST 1.1
 | (n=93) | (n=19)
Median DOR in months (95% CI) | NE (NE, NE) | 6.3 (4.7, NE)
Range (months) | (1.3 [Denotes a censored value] , 13.4) | (1.4, 9.1)
Overall Response Rate, (ORR), HCC mRECIST
Number of responders (%) | 112 (33) | 21 (13)
(95% CI) | (28, 39) | (8, 19)
p-value | <0.0001
Complete responses, n (%) | 37 (11) | 3 (1.8)
Partial responses, n (%) | 75 (22) | 18 (11)
Duration of Response, (DOR) HCC mRECIST
 | (n=112) | (n=21)
Median DOR in months (95% CI) | NE (NE, NE) | 6.3 (4.9, NE)
Range (months) | (1.3, 13.4) | (1.4, 9.1)
CI=confidence interval; HCC mRECIST=Modified RECIST Assessment for Hepatocellular Carcinoma; NE=not estimable; RECIST 1.1=Response Evaluation Criteria in Solid Tumors v1.1

Figure 9: Kaplan-Meier Plot of Overall Survival in IMbrave150

Exploratory analyses showed that the subset of patients (20%) who were ADA-positive by week 6 appeared to have reduced efficacy (effect on OS) as compared to patients (80%) who tested negative for treatment-emergent ADA by week 6 [see Clinical Pharmacology (12.6)]. ADA-positive patients by week 6 appeared to have similar overall survival compared to sorafenib-treated patients. In an exploratory analysis, inverse probability weighting was conducted to compare ADA-positive patients and ADA-negative patients in the TECENTRIQ and bevacizumab arm to the sorafenib arm. Inverse probability weighting factors were: baseline sum of longest tumor size (BSLD), baseline ECOG, baseline albumin, baseline LDH, sex, age, race, geographic region, weight, neutrophil-to-lymphocyte ratio, AFP (<400 ng/mL vs ≥400 ng/mL), number of metastatic sites, MVI and/or EHS present at study entry, etiology (HBV vs. HCV vs. non-viral) and Child-Pugh Score (A5 vs. A6). The OS hazard ratio comparing the ADA-positive subgroup of the TECENTRIQ and bevacizumab arm to sorafenib was 0.93 (95% CI: 0.57, 1.53). The OS hazard ratio comparing the ADA-negative subgroup to sorafenib was 0.39 (95% CI: 0.26, 0.60).

14.4 Melanoma

The efficacy of TECENTRIQ in combination with cobimetinib and vemurafenib was evaluated in a double-blind, randomized (1:1), placebo-controlled, multicenter trial (IMspire150; NCT02908672) conducted in 514 patients. Randomization was stratified by geographic location (North America vs. Europe vs. Australia, New Zealand, and others) and baseline lactate dehydrogenase (LDH) [less than or equal to upper limit of normal (ULN) vs. greater than ULN]. Eligible patients were required to have previously untreated unresectable or metastatic BRAF V600 mutation-positive melanoma as detected by a locally available test and centrally confirmed with the FoundationOne™ assay. Patients were excluded if they had history of autoimmune disease; administration of a live, attenuated vaccine within 28 days prior to randomization; administration of systemic immunostimulatory agents within 4 weeks or systemic immunosuppressive medications within 2 weeks prior to randomization; and active or untreated CNS metastases.

TECENTRIQ was initiated after patients received a 28-day treatment cycle of cobimetinib 60 mg orally once daily (21 days on / 7 days off) and vemurafenib 960 mg orally twice daily Days 1-21 and 720 mg orally twice daily Days 22-28. Patients received TECENTRIQ 840 mg intravenous infusion over 60 minutes every 2 weeks in combination with cobimetinib 60 mg orally once daily and vemurafenib 720 mg orally twice daily, or placebo in combination with cobimetinib 60 mg orally once daily and vemurafenib 960 mg orally twice daily. Treatment continued until disease progression or unacceptable toxicity. There was no crossover at the time of disease progression. Tumor assessments were performed every 8 weeks (± 1 week) for the first 24 months and every 12 weeks (± 1 week) thereafter.

The major efficacy outcome measure was investigator-assessed progression-free survival (PFS) per RECIST v1.1. Additional efficacy outcomes included PFS assessed by an independent central review, investigator-assessed ORR, OS, and DOR.

The median age of the study population was 54 years (range: 22-88), 58% of patients were male, 95% were White, a baseline ECOG performance status of 0 (77%) or 1 (23%), 33% had elevated LDH, 94% had metastatic disease, 60% were Stage IV (M1C), 56% had less than three metastatic sites at baseline, 3% had prior treatment for brain metastases, 30% had liver metastases at baseline, and 14% had received prior adjuvant systemic therapy. Based on central testing, 74% were identified as having a V600E mutation, 11% as having V600K mutation, and 1% as having V600D or V600R mutations.

Efficacy results are summarized in Table 32 and Figure 10. Patients had a median survival follow up time of 18.9 months.

Table 32: Efficacy Results from IMspire150
 | TECENTRIQ + Cobimetinib + Vemurafenib N=256 | Placebo + Cobimetinib + Vemurafenib N=258
Progression-Free Survival [As determined by investigator assessment with Response Evaluation Criteria in Solid Tumors v1.1.; CI=confidence interval;]
Number of events (%) | 148 (58) | 179 (69)
Median, months | 15.1 | 10.6
(95% CI) | (11.4, 18.4) | (9.3, 12.7)
Hazard ratio [Stratified by baseline LDH] (95% CI) | 0.78 (0.63, 0.97)
p-value [Based on the stratified log-rank test] | 0.0249
Overall Response Rate, [Confirmed Responses]
Number of responders (%) | 170 (66) | 168 (65)
(95% CI) | (60, 72) | (59, 71)
Complete responses, n (%) | 41 (16) | 46 (18)
Partial response, n (%) | 129 (50) | 122 (47)
Duration of Response, | n=170 | n=168
Median, months | 20.4 | 12.5
(95% CI) | (15.1, NE) | (10.7, 16.6)

Figure 10: Kaplan-Meier Plot for Progression-Free Survival in IMspire150

At a pre-specified analysis at the time of the primary analysis of PFS, the OS data were not mature. The median OS was 28.8 months with 93 (36%) deaths in the TECENTRIQ plus cobimetinib and vemurafenib arm, and 25.1 months with 112 (43%) deaths in the placebo plus cobimetinib and vemurafenib arm. The hazard ratio for OS was 0.85 (95% CI: 0.64, 1.11) and the p-value was 0.2310.

14.5 Alveolar soft part sarcoma (ASPS)

The efficacy of TECENTRIQ was evaluated in study ML39345 (NCT03141684), an open-label, single-arm study, in 49 adult and pediatric patients aged 2 years and older with unresectable or metastatic ASPS. Eligible patients were required to have histologically or cytologically confirmed ASPS that was not curable by surgery, and an ECOG performance status of ≤ 2.

Patients were excluded if they had known primary central nervous system (CNS) malignancy or symptomatic CNS metastases, known clinically significant liver disease, or history of idiopathic pulmonary fibrosis, pneumonitis, organizing pneumonia, or evidence of active pneumonitis on screening chest computed tomography (CT) scan.

Adult patients received 1200 mg intravenously and pediatric patients received 15 mg/kg (up to a maximum of 1200 mg) intravenously once every 21 days until disease progression or unacceptable toxicity.

The major efficacy outcomes were Overall Response Rate (ORR) and Duration of Response (DOR) by Independent Review Committee according to Response Evaluation Criteria in Solid Tumors (RECIST) v1.1.

A total of 49 patients were enrolled. The median age of patients was 31 years (range: 12-70); 2% of adult patients (n=47) were ≥65 years of age and the pediatric patients (n=2) were ≥12 years of age; 51% of patients were female, 55% White, 29% Black or African American, 10% Asian; 53% had an ECOG performance status of 0 and 45% had an ECOG performance status of 1. All patients had prior surgery for ASPS and 55% received at least one prior line of treatment for ASPS; 55% received radiotherapy and 53% received chemotherapy. Of the patients who reported staging at initial diagnosis, all were Stage IV.

Efficacy results of this study are summarized in Table 33.

Table 33: Efficacy Results from Study ML39345
Endpoint | All Patients (N=49)
Overall response rate (95% CI) [95% CI based on Clopper–Pearson exact method.] | 24% (13, 39)
Complete Responses, n | 0
Partial Responses, n (%) | 12 (24)
Duration of response
Median, month | NE
(95% CI) | (17.0, NE)
Range | 1+, 41+
Durability of Response
≥6 months, n (%) | 8 (67%)
≥12 months, n (%) | 5 (42%)
CI: confidence interval; N: number of patients; +: Censored

16 HOW SUPPLIED/STORAGE AND HANDLING

TECENTRIQ injection is a sterile, preservative-free, and colorless to slightly yellow solution for intravenous infusion supplied as a carton containing one 840 mg/14 mL single-dose vial (NDC 50242-918-01) or 1,200 mg/20 mL single-dose vial (NDC 50242-917-01).

STORAGE AND HANDLING

Store vials under refrigeration at 2°C to 8°C (36°F to 46°F) in original carton to protect from light. Do not freeze. Do not shake.

17 PATIENT COUNSELING INFORMATION

Advise the patient to read the FDA-approved patient labeling (Medication Guide).

Immune-Mediated Adverse Reactions

Inform patients of the risk of immune-mediated adverse reactions that may require corticosteroid treatment and interruption or discontinuation of TECENTRIQ, including:

- Pneumonitis: Advise patients to contact their healthcare provider immediately for any new or worsening cough, chest pain, or shortness of breath [see Warnings and Precautions (5.1)].
- Colitis: Advise patients to contact their healthcare provider immediately for diarrhea, blood or mucus in stools, or severe abdominal pain [see Warnings and Precautions (5.1)].
- Hepatitis: Advise patients to contact their healthcare provider immediately for jaundice, severe nausea or vomiting, pain on the right side of abdomen, lethargy, or easy bruising or bleeding [see Warnings and Precautions (5.1)].
- Endocrinopathies: Advise patients to contact their healthcare provider immediately for signs or symptoms of hypophysitis, hyperthyroidism, hypothyroidism, adrenal insufficiency, or type 1 diabetes mellitus, including diabetic ketoacidosis [see Warnings and Precautions (5.1)].
- Nephritis: Advise patients to contact their healthcare provider immediately for pelvic pain, frequent urination, or unusual swelling. [see Warnings and Precautions (5.1)].
- Dermatologic Adverse Reactions: Advise patients to contact their healthcare provider immediately for generalized rash, skin eruption, or painful skin and mucous membrane lesions [see Warnings and Precautions (5.1)].
- Other Immune-Mediated Adverse Reactions: Advise patients to contact their healthcare provider immediately for signs or symptoms of other potential immune-mediated adverse reactions [see Warnings and Precautions (5.1)].

Infusion-Related Reactions

Advise patients to contact their healthcare provider immediately for signs or symptoms of infusion-related reactions [see Warnings and Precautions (5.2)].

Complications of Allogeneic HSCT after PD-1/PD-L1 inhibitors

Follow patients closely for evidence of transplant-related complications and intervene promptly. Consider the benefits versus risks of treatment with a PD-1/PD-L1 blocking antibody prior to or after an allogeneic HSCT [see Warnings and Precautions (5.3)].

Embryo-Fetal Toxicity

Advise females of reproductive potential that TECENTRIQ can cause harm to a fetus and to inform their healthcare provider of a known or suspected pregnancy [see Warnings and Precautions (5.4), Use in Specific Populations (8.1, 8.3)].

Advise females of reproductive potential to use effective contraception during treatment and for at least 5 months after the last dose of TECENTRIQ [see Use in Specific Populations (8.3)].

Lactation

Advise female patients not to breastfeed while taking TECENTRIQ and for at least 5 months after the last dose [see Use in Specific Populations (8.2)].

Manufactured by:
Genentech, Inc.
A Member of the Roche Group
1 DNA Way
South San Francisco, CA 94080-4990

U.S. License No.: 1048

TECENTRIQ is a registered trademark of Genentech, Inc.
©2025 Genentech, Inc.

MEDICATION GUIDE
TECENTRIQ® (te-SEN-trik)
(atezolizumab)
Injection

What is the most important information I should know about TECENTRIQ?

TECENTRIQ is a medicine that may treat certain cancers by working with your immune system. TECENTRIQ can cause your immune system to attack normal organs and tissues in any area of your body and can affect the way they work. These problems can sometimes become severe or life-threatening and can lead to death. You can have more than one of these problems at the same time. These problems may happen anytime during your treatment or even after your treatment has ended.

Call or see your healthcare provider right away if you develop any new or worse signs or symptoms, including: Lung problems.

- cough

- shortness of breath

- chest pain

Intestinal problems.

- diarrhea (loose stools) or more frequent bowel movements than usual
- stools that are black, tarry, sticky, or have blood or mucus
- severe stomach-area (abdomen) pain or tenderness

Liver problems.

- yellowing of your skin or the whites of your eyes
- severe nausea or vomiting
- pain on the right side of your stomach area (abdomen)

- dark urine (tea colored)
- bleeding or bruising more easily than normal

Hormone gland problems.

- headaches that will not go away or unusual headaches
- eye sensitivity to light
- eye problems
- rapid heart beat
- increased sweating
- extreme tiredness
- weight gain or weight loss
- feeling more hungry or thirsty than usual

- urinating more often than usual
- hair loss
- feeling cold
- constipation
- your voice gets deeper
- dizziness or fainting
- changes in mood or behavior, such as decreased sex drive, irritability, or forgetfulness

Kidney problems.

- decrease in your amount of urine
- blood in your urine

- swelling of your ankles
- loss of appetite

Skin problems.

- rash
- itching
- skin blistering or peeling

- painful sores or ulcers in mouth or nose, throat, or genital area
- fever or flu-like symptoms
- swollen lymph nodes

Problems can also happen in other organs.
These are not all of the signs and symptoms of immune system problems that can happen with TECENTRIQ. Call or see your healthcare provider right away for any new or worse signs or symptoms, including:

- chest pain, irregular heartbeat, shortness of breath, or swelling of ankles
- confusion, sleepiness, memory problems, changes in mood or behavior, stiff neck, balance problems, tingling or numbness of the arms or legs
- double vision, blurry vision, sensitivity to light, eye pain, changes in eyesight
- persistent or severe muscle pain or weakness, muscle cramps
- low red blood cells, bruising

Infusion reactions that can sometimes be severe or life-threatening. Signs and symptoms of infusion reactions may include:

- chills or shaking
- itching or rash
- flushing
- shortness of breath or wheezing

- dizziness
- feeling like passing out
- fever
- back or neck pain

Complications, including graft-versus-host disease (GVHD), in people who have received a bone marrow (stem cell) transplant that uses donor stem cells (allogeneic). These complications can be serious and can lead to death. These complications may happen if you underwent transplantation either before or after being treated with TECENTRIQ. Your healthcare provider will monitor you for these complications.

Getting medical treatment right away may help keep these problems from becoming more serious.
Your healthcare provider will check you for these problems during your treatment with TECENTRIQ. Your healthcare provider may treat you with corticosteroid or hormone replacement medicines. Your healthcare provider may also need to delay or completely stop treatment with TECENTRIQ if you have severe side effects.

What is TECENTRIQ?

TECENTRIQ is a prescription medicine used to treat:

- adults with a type of lung cancer called non-small cell lung cancer (NSCLC).
  - TECENTRIQ may be used alone as a treatment for your lung cancer:
    - to help prevent your lung cancer from coming back after your tumor(s) has been removed by surgery and you have received platinum-based chemotherapy, and
    - you have stage 2 to stage 3A NSCLC (talk to your healthcare provider about what these stages mean), and
    - your cancer tests positive for "PD-L1".
  - TECENTRIQ may be used alone as your first treatment when your lung cancer:
    - has spread or grown, and
    - your cancer tests positive for "high PD-L1", and
    - your tumor does not have an abnormal "EGFR" or "ALK" gene.
  - TECENTRIQ may be used with the medicines bevacizumab, paclitaxel, and carboplatin as your first treatment when your lung cancer:
    - has spread or grown, and
    - is a type called "non-squamous NSCLC", and
    - your tumor does not have an abnormal "EGFR" or "ALK" gene.
  - TECENTRIQ may be used with the medicines paclitaxel protein-bound and carboplatin as your first treatment when your lung cancer:
    - has spread or grown, and
    - is a type called "non-squamous NSCLC", and
    - your tumor does not have an abnormal "EGFR" or "ALK" gene.
  - TECENTRIQ may also be used alone when your lung cancer:
    - has spread or grown, and
    - you have tried chemotherapy that contains platinum, and it did not work or is no longer working.
    - if your tumor has an abnormal "EGFR" or "ALK" gene, you should have also tried an FDA-approved therapy for tumors with these abnormal genes, and it did not work or is no longer working.
- adults with a type of lung cancer called "extensive-stage small cell lung cancer (SCLC)", which is SCLC that has spread or grown.
  - TECENTRIQ may be used with the chemotherapy medicines carboplatin and etoposide as your first treatment.
  - TECENTRIQ may be used with the medicine lurbinectedin as maintenance treatment when your lung cancer:
    - has not progressed after first treatment with TECENTRIQ or atezolizumab and hyaluronidase-tqjs and the chemotherapy medicines carboplatin and etoposide.
- adults with a type of liver cancer called hepatocellular carcinoma (HCC). TECENTRIQ may be used with the medicine bevacizumab when your liver cancer:
  - has spread or cannot be removed by surgery, and
  - you have not received other medicines by mouth or injection through your vein (IV) to treat your cancer.
- adults with a type of skin cancer called melanoma. TECENTRIQ may be used with the medicines cobimetinib and vemurafenib when your melanoma:
  - has spread to other parts of the body or cannot be removed by surgery, and
  - has a certain type of abnormal "BRAF" gene. Your healthcare provider will perform a test to make sure this TECENTRIQ combination is right for you.
- adults and children 2 years of age and older with a type of soft tissue tumor (cancer) called alveolar soft part sarcoma (ASPS). TECENTRIQ may be used when your sarcoma:
  - has spread to other parts of the body or cannot be removed by surgery.

It is not known if TECENTRIQ is safe and effective when used:

- in children younger than 2 years of age for the treatment of ASPS.
- in children for the treatment of NSCLC, SCLC, HCC, or melanoma.

Before receiving TECENTRIQ, tell your healthcare provider about all of your medical conditions, including if you:

- have immune system problems such as Crohn's disease, ulcerative colitis, or lupus
- have received an organ transplant
- have received or plan to receive a stem cell transplant that uses donor stem cells (allogeneic)
- have received radiation treatment to your chest area
- have a condition that affects your nervous system, such as myasthenia gravis or Guillain-Barré syndrome
- are pregnant or plan to become pregnant. TECENTRIQ can harm your unborn baby. Tell your healthcare provider right away if you become pregnant or think you may be pregnant during treatment with TECENTRIQ.
  Females who are able to become pregnant:
  - Your healthcare provider should do a pregnancy test before you start treatment with TECENTRIQ.
  - You should use an effective method of birth control during your treatment and for at least 5 months after the last dose of TECENTRIQ.
- are breastfeeding or plan to breastfeed. It is not known if TECENTRIQ passes into your breast milk. Do not breastfeed during treatment and for at least 5 months after the last dose of TECENTRIQ.

Tell your healthcare provider about all the medicines you take, including prescription and over-the-counter medicines, vitamins, and herbal supplements.

How will I receive TECENTRIQ?

- Your healthcare provider will give you TECENTRIQ into your vein through an intravenous (IV) line over 30 to 60 minutes.
- TECENTRIQ is usually given every 2, 3, or 4 weeks.
- Your healthcare provider will decide how many treatments you need.
- Your healthcare provider will test your blood to check you for certain side effects.
- For treatment of a type of skin cancer called melanoma, your healthcare provider will also prescribe you cobimetinib and vemurafenib. Take cobimetinib and vemurafenib exactly as your healthcare provider tells you.
- If you miss any appointments, call your healthcare provider as soon as possible to reschedule your appointment.

What are the possible side effects of TECENTRIQ?

TECENTRIQ can cause serious side effects, including:

- See "What is the most important information I should know about TECENTRIQ?"

The most common side effects of TECENTRIQ when used alone include:

- feeling tired or weak
- decreased appetite

- nausea
- cough

- shortness of breath

The most common side effects of TECENTRIQ when used in lung cancer with other anti-cancer medicines include:

- feeling tired or weak
- nausea

- hair loss
- constipation

- diarrhea
- decreased appetite

The most common side effects of TECENTRIQ when used in hepatocellular carcinoma with bevacizumab include:

- high blood pressure

- feeling tired or weak

- too much protein in the urine

The most common side effects of TECENTRIQ when used in melanoma with cobimetinib and vemurafenib include:

- skin rash
- joint, muscle, or bone pain
- feeling tired or weak
- liver injury

- fever
- nausea
- itching
- swelling of legs or arms

- mouth swelling (sometimes with sores)
- low thyroid hormone levels
- sunburn or sun sensitivity

TECENTRIQ may cause fertility problems in females, which may affect the ability to have children. Talk to your healthcare provider if you have concerns about fertility.

These are not all the possible side effects of TECENTRIQ.

Call your doctor for medical advice about side effects. You may report side effects to FDA at 1-800-FDA-1088.

General information about the safe and effective use of TECENTRIQ.

Medicines are sometimes prescribed for purposes other than those listed in a Medication Guide. You can ask your pharmacist or healthcare provider for information about TECENTRIQ that is written for health professionals.

What are the ingredients in TECENTRIQ?

Active ingredient: atezolizumab

Inactive ingredients: glacial acetic acid, L-histidine, polysorbate 20 and sucrose

Manufactured by: Genentech, Inc., A Member of the Roche Group, 1 DNA Way, South San Francisco, CA 94080-4990 USA

U.S. License No.: 1048 TECENTRIQ is a registered trademark of Genentech, Inc.

For more information, call 1-844-832-3687 or go to www.TECENTRIQ.com.

This Medication Guide has been approved by the U.S. Food and Drug Administration.

Revised: 10/2025

Representative sample of labeling (see the HOW SUPPLIED section for complete listing):

PRINCIPAL DISPLAY PANEL - 20 mL Vial Carton

NDC 50242-917-01

Tecentriq®
(atezolizumab)
Injection

1200 mg/20 mL
(60 mg/mL)

For Intravenous Infusion After Dilution
Single-Dose Vial
Discard Unused Portion
No preservative.

Attention Pharmacist: Dispense the
accompanying Medication Guide
to each patient.

1 vial

Rx only

Genentech

10199144

PRINCIPAL DISPLAY PANEL - 14 mL Vial Carton

NDC 50242-918-01

Tecentriq®
(atezolizumab)
Injection

840 mg/14 mL
(60 mg/mL)

For Intravenous Infusion After Dilution
Single-Dose Vial
Discard Unused Portion
No preservative.

Attention Pharmacist: Dispense the
accompanying Medication Guide
to each patient.

1 vial

Rx only
Genentech

10198487